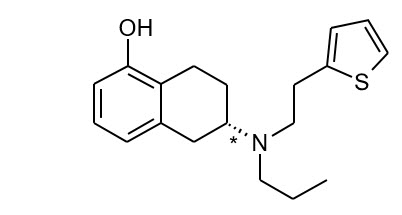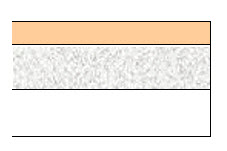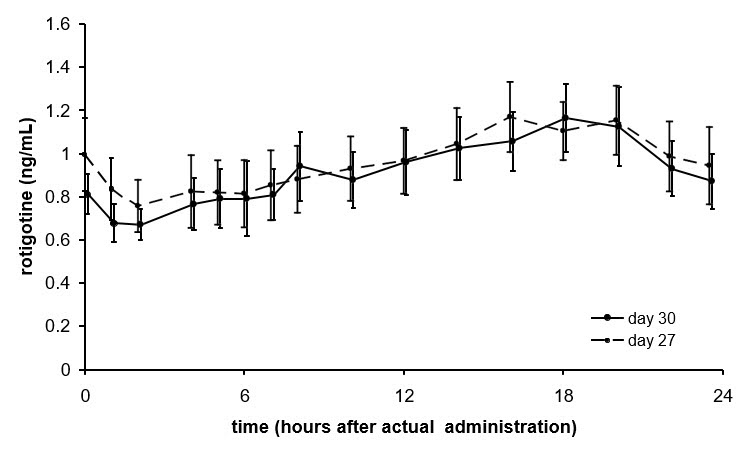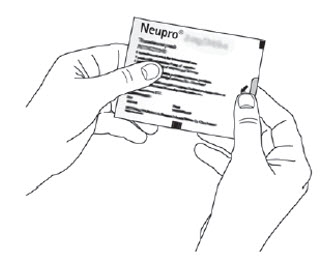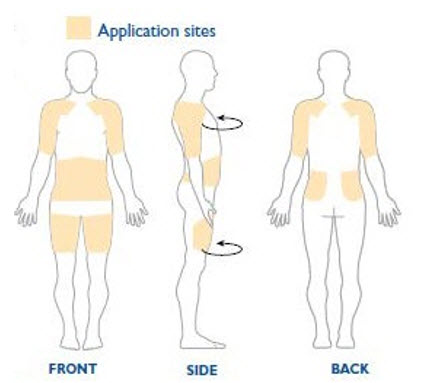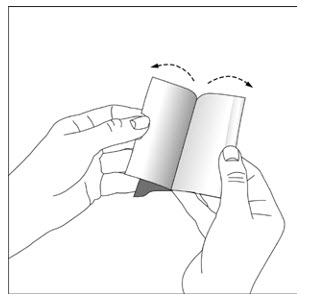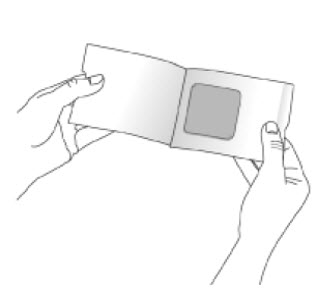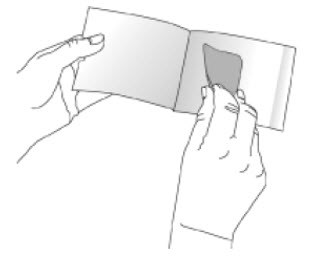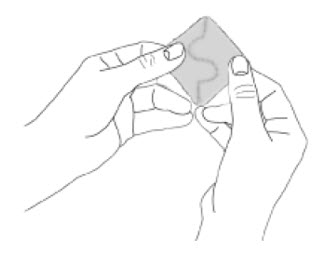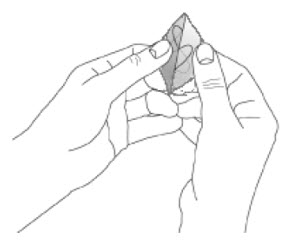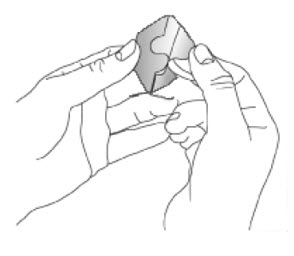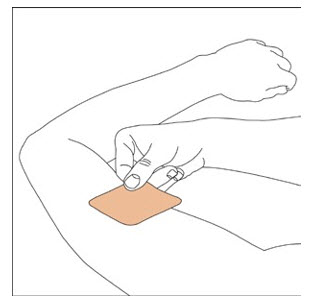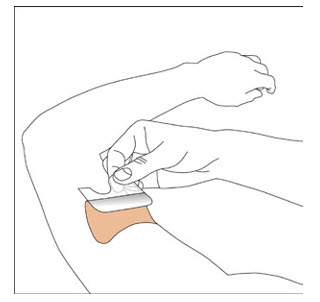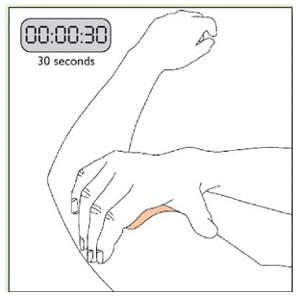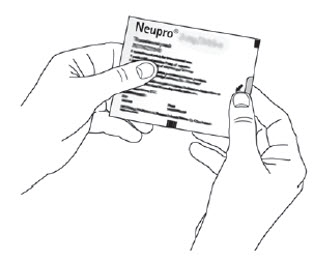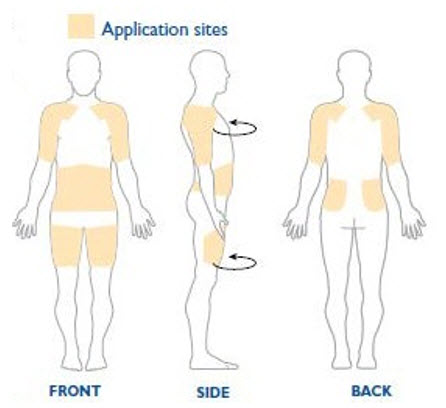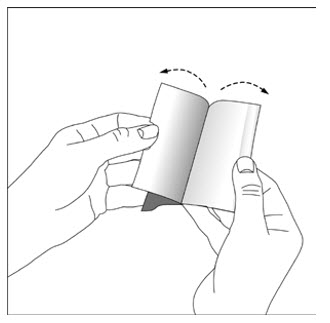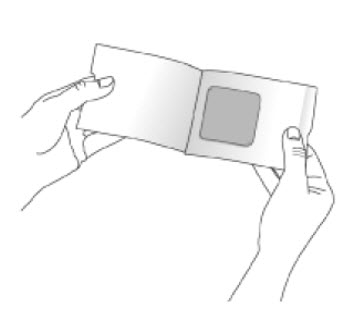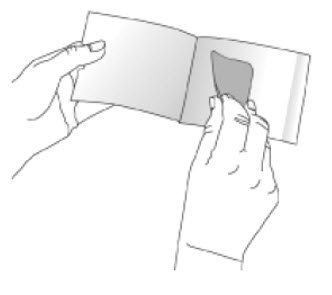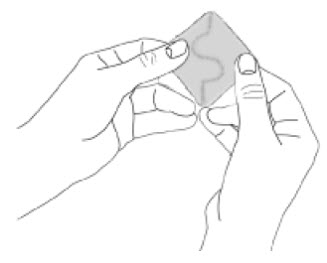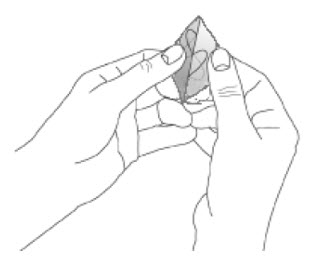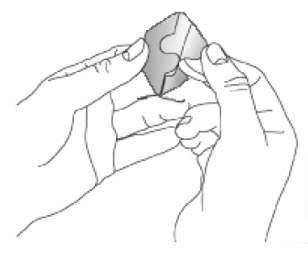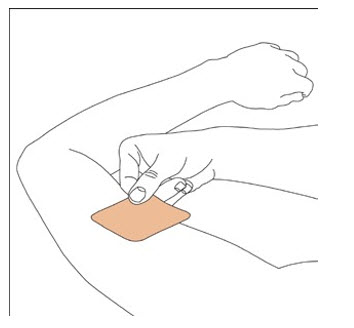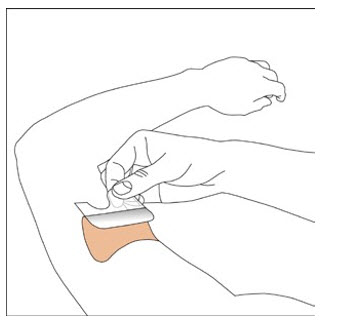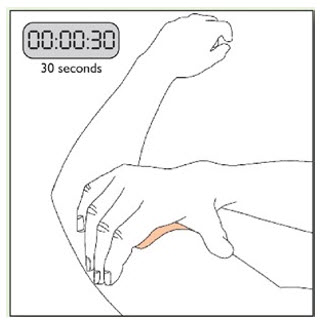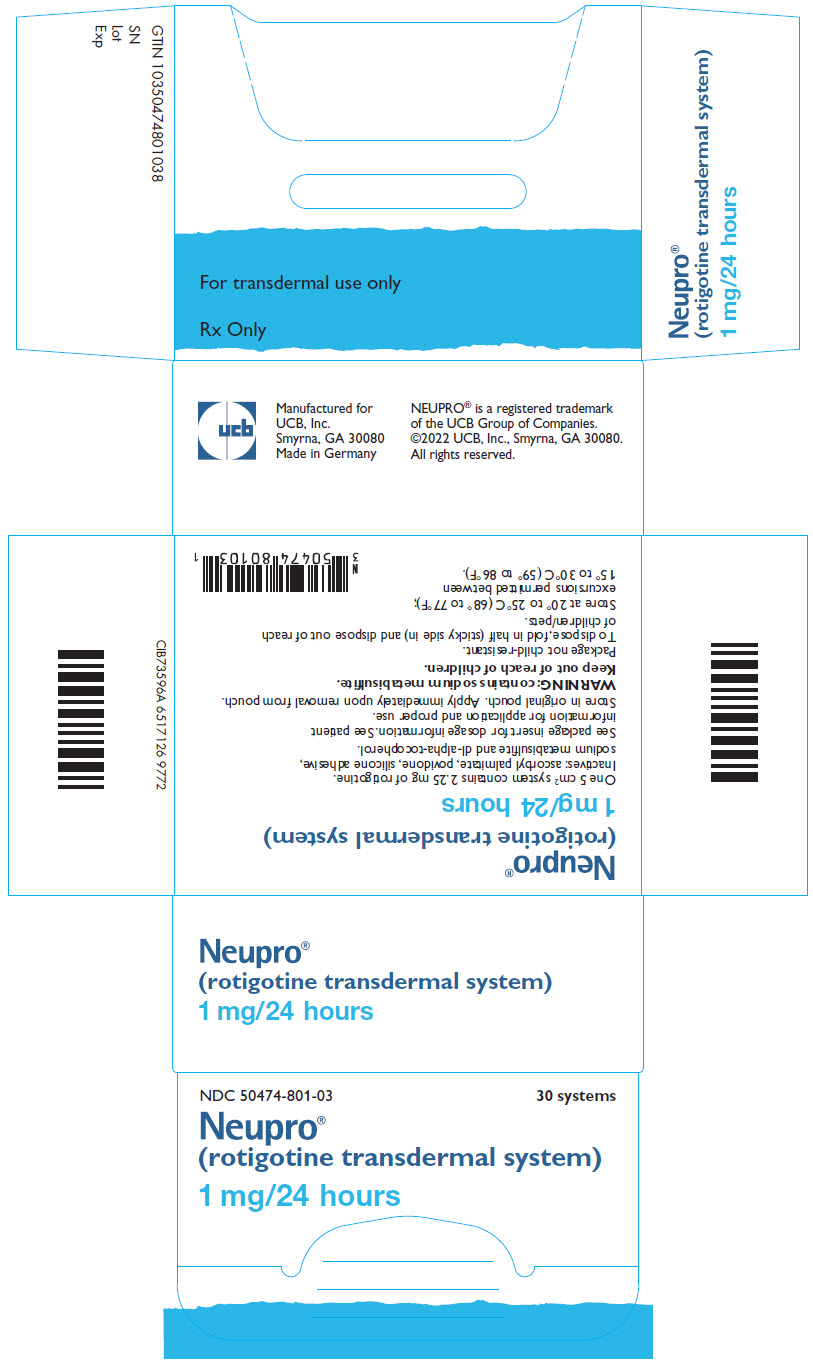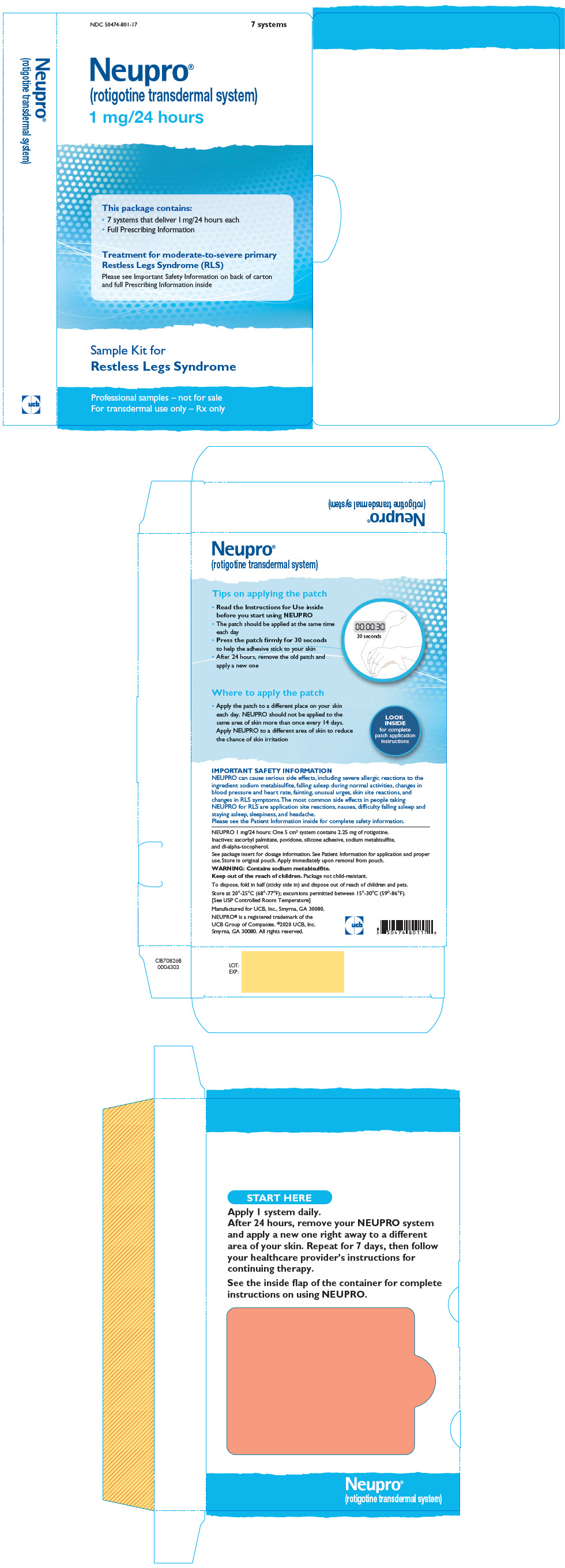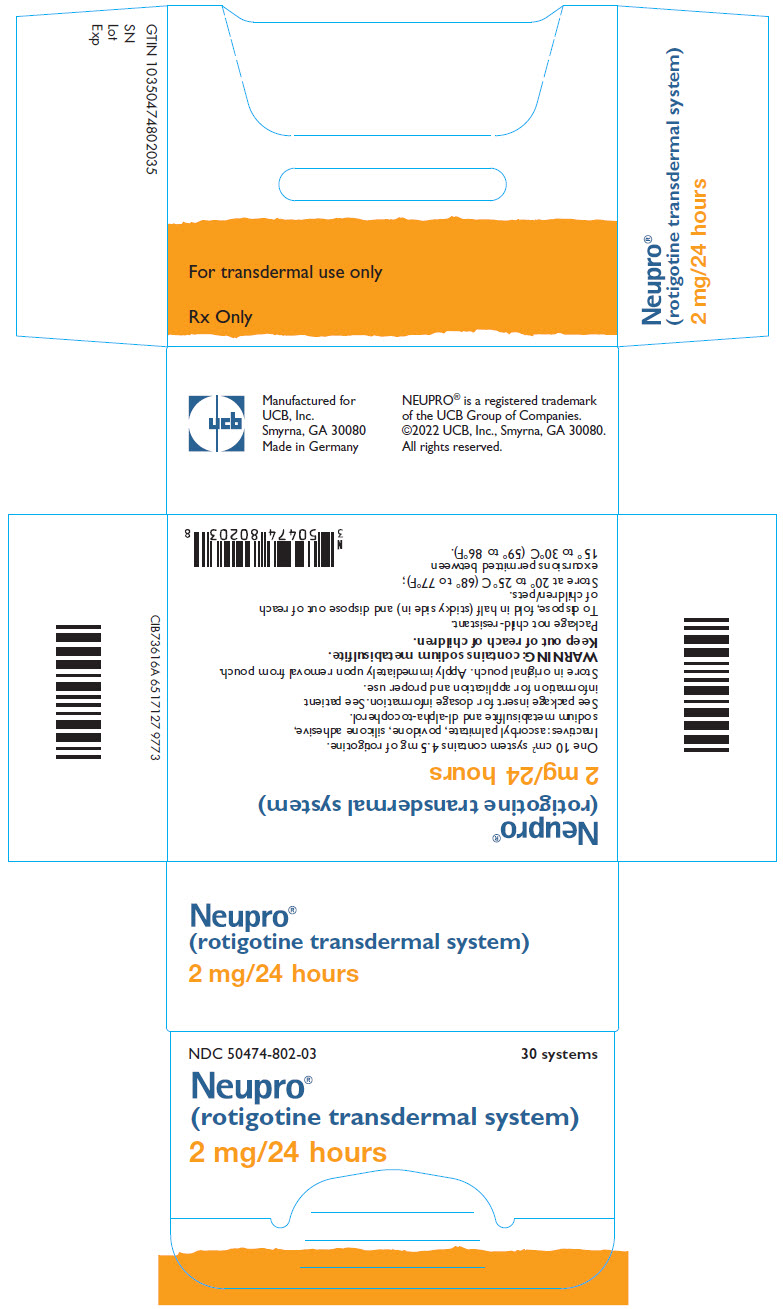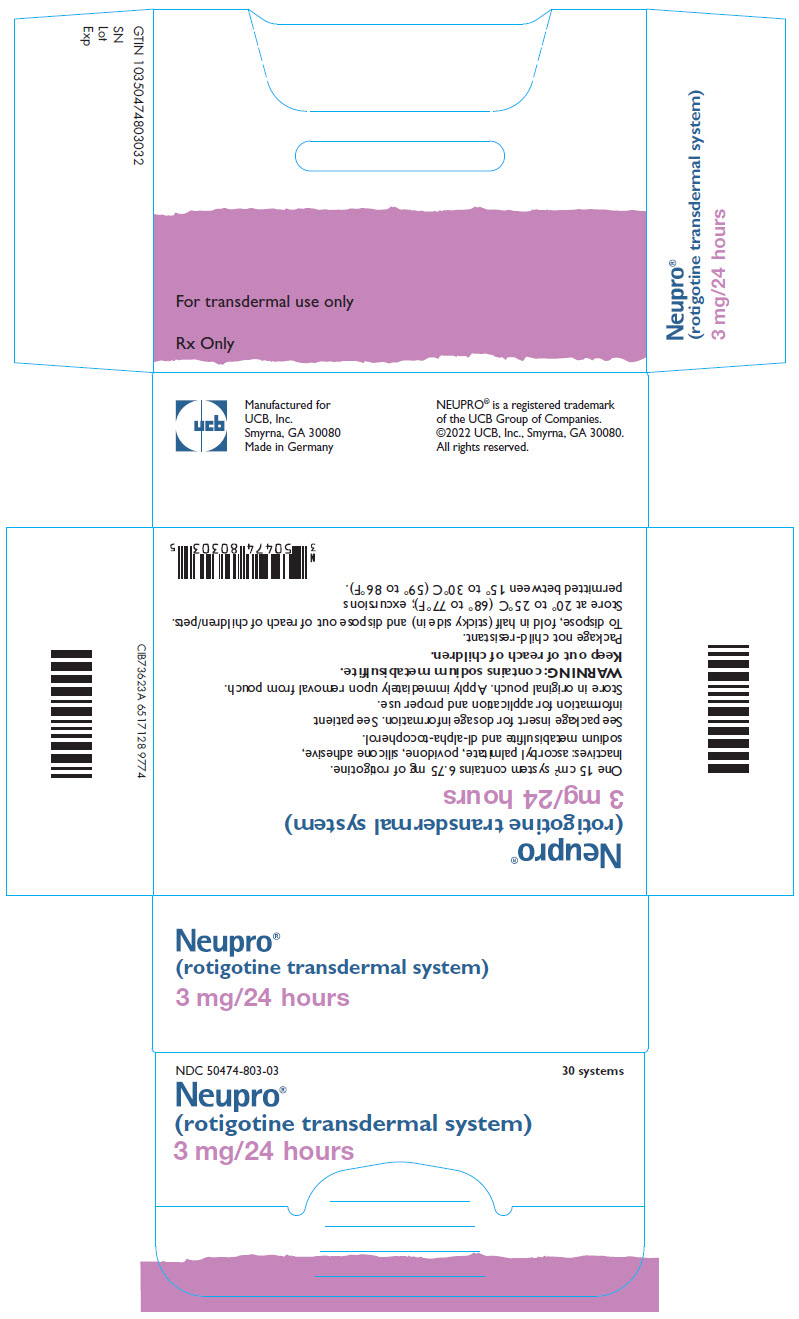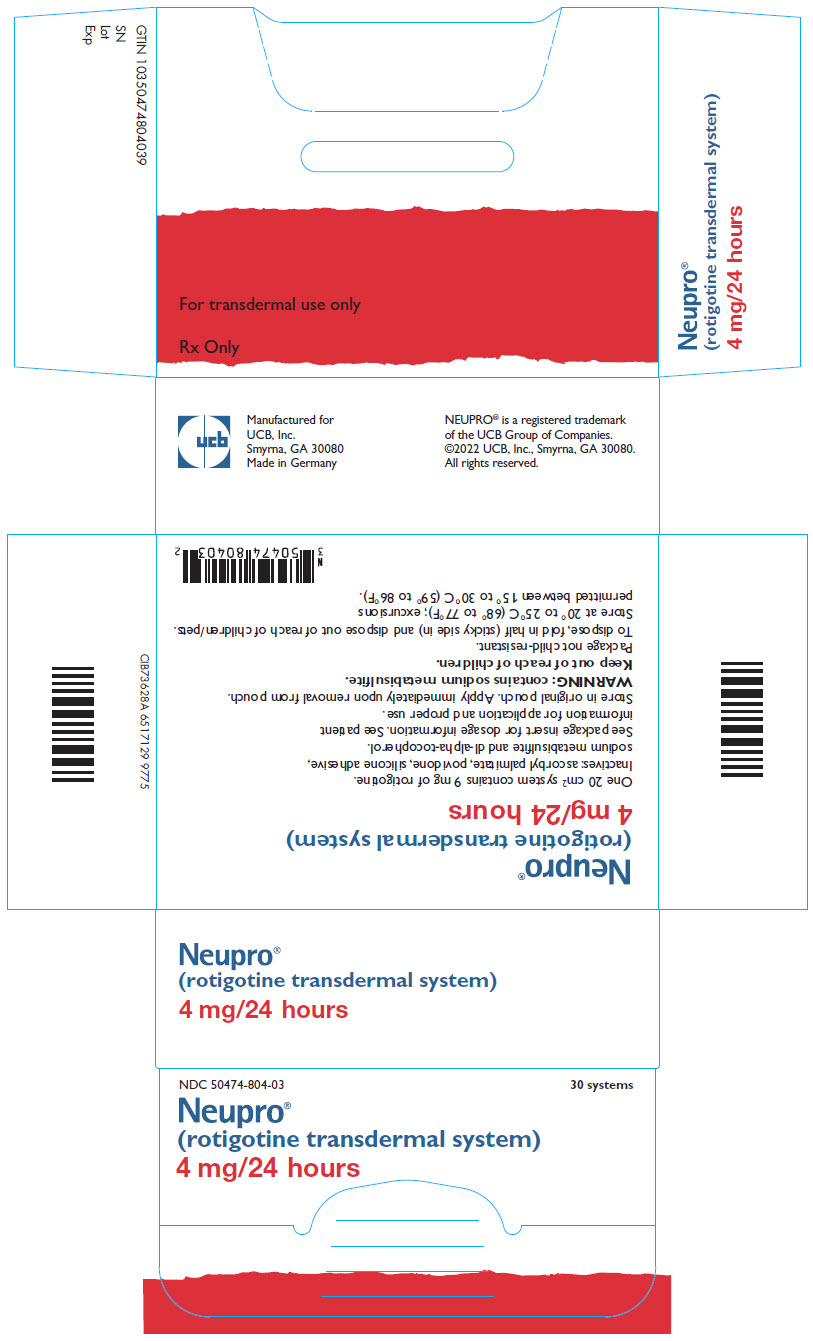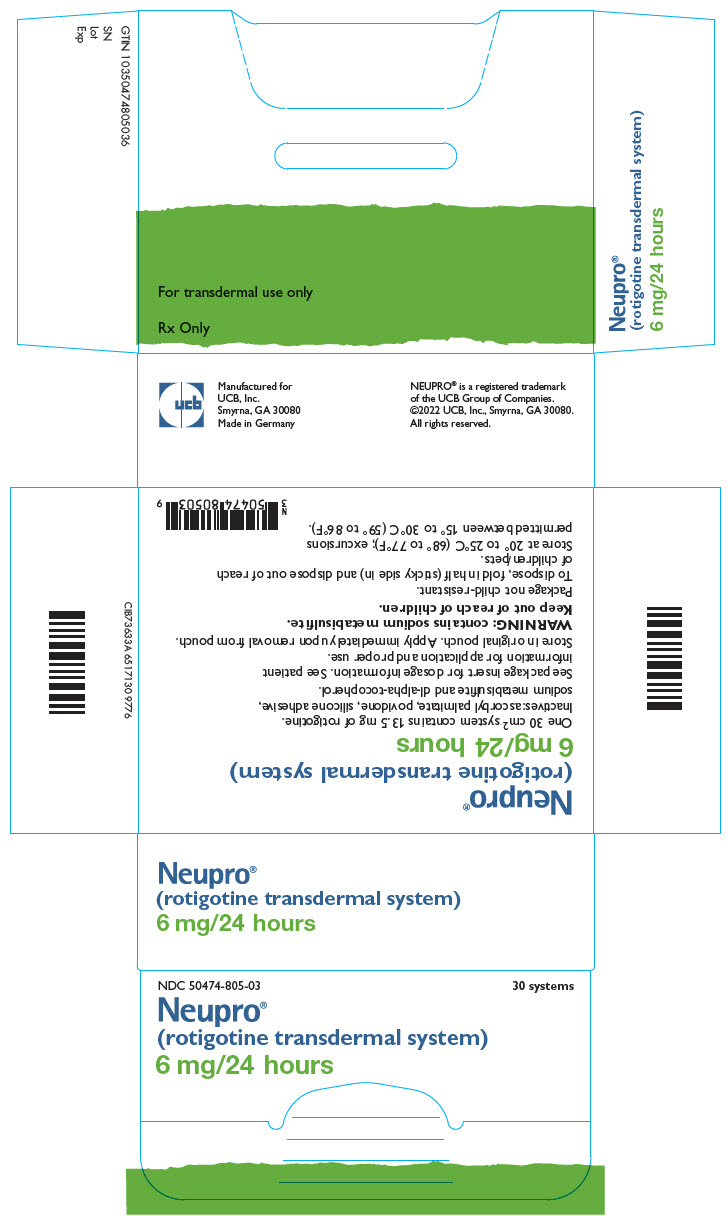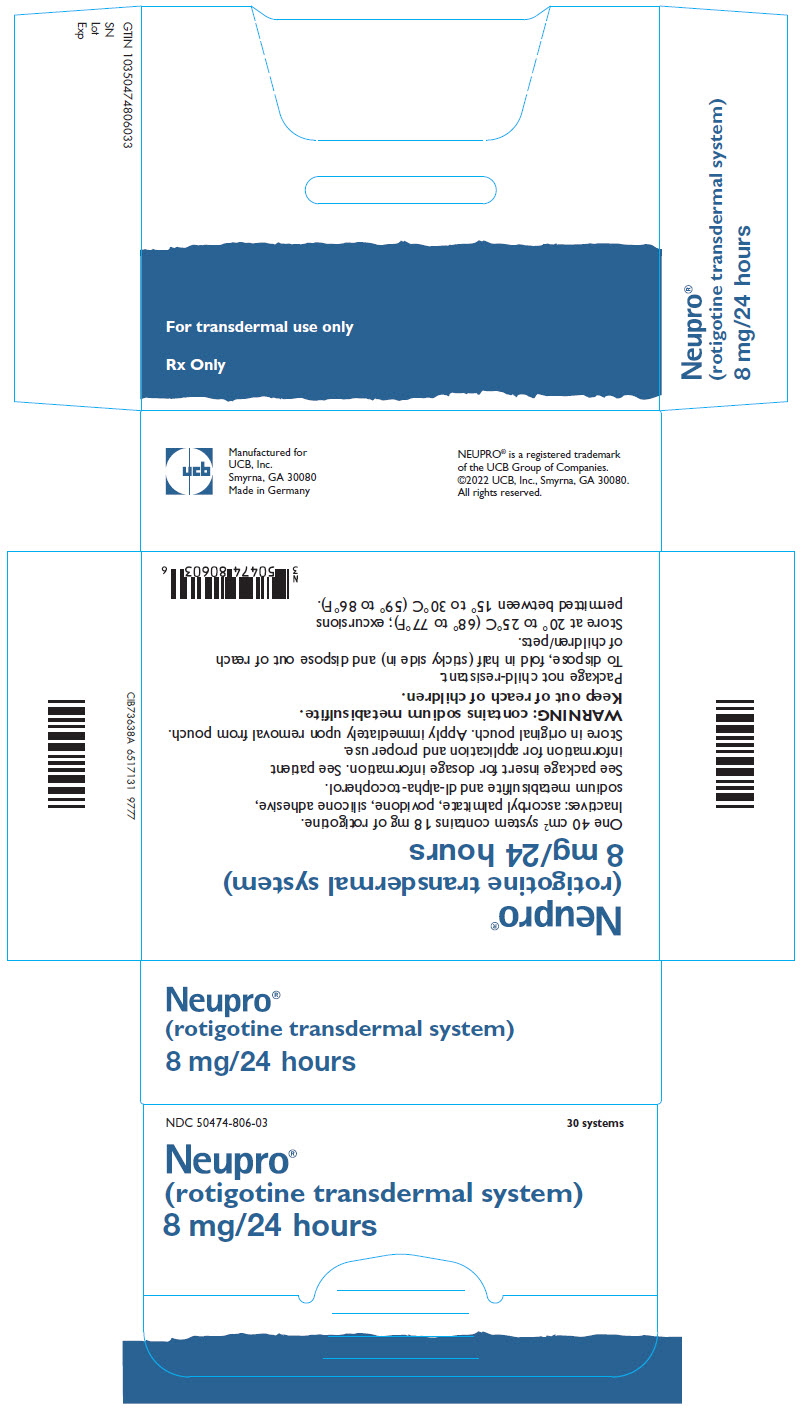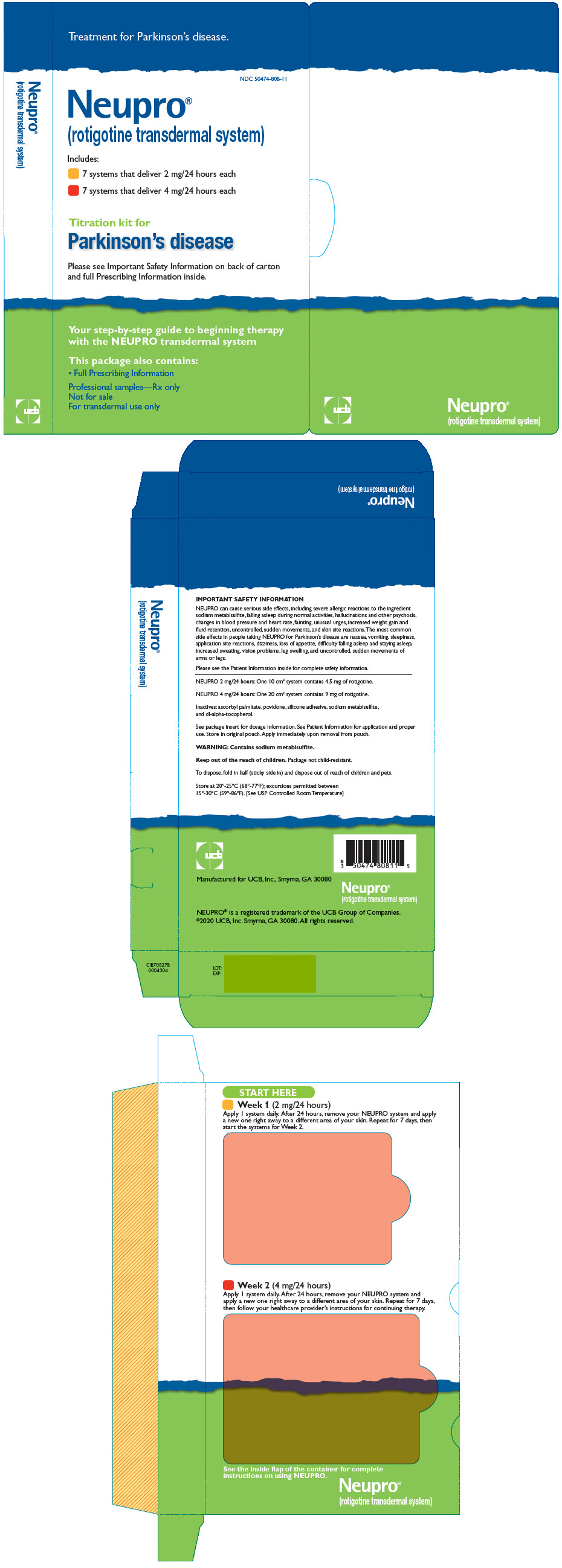 DRUG LABEL: Neupro
NDC: 50474-801 | Form: PATCH, EXTENDED RELEASE
Manufacturer: UCB, Inc.
Category: prescription | Type: HUMAN PRESCRIPTION DRUG LABEL
Date: 20250624

ACTIVE INGREDIENTS: ROTIGOTINE 1 mg/24 h
INACTIVE INGREDIENTS: ASCORBYL PALMITATE; POVIDONE, UNSPECIFIED; SODIUM METABISULFITE; .ALPHA.-TOCOPHEROL, DL-

HIGHLIGHTS OF PRESCRIBING INFORMATION

These highlights do not include all the information needed to use NEUPRO safely and effectively. See full prescribing information for NEUPRO.
NEUPRO (rotigotine transdermal system)
Initial U.S. Approval: 2007

RECENT MAJOR CHANGES

Warnings and Precautions, Impulse Control/Compulsive Behaviors (5.6) | 7/2021
Warnings and Precautions, Withdrawal Symptoms (5.15) | 7/2021

1 INDICATIONS AND USAGE

NEUPRO is a dopamine agonist indicated for the treatment of:

- Parkinson's disease (1.1)
- Moderate-to-severe primary Restless Legs Syndrome (1.2)

2 DOSAGE AND ADMINISTRATION

- Parkinson's disease:Initially, 2 mg/24 hours for early-stage disease or 4 mg/24 hours for advanced-stage disease. The dose may be increased as needed by 2 mg/24 hours at weekly intervals, up to 6 mg/24 hours for early-stage disease and up to 8 mg/24 hours for advanced-stage disease. (2.1)
- Restless Legs Syndrome:Initially, 1 mg/24 hours, increased as needed by 1 mg/24 hours at weekly intervals, up to 3 mg/24 hours. (2.2)
- Apply once a day to the skin; press firmly in place for 30 seconds. Do not place NEUPRO on oily, irritated, or damaged skin, or where it will be rubbed by tight clothing. Do not use the same site more than once every 14 days. The prescribed dose may be achieved using single or multiple patches. (2.3)
- To discontinue treatment, reduce the dose gradually until complete withdrawal of NEUPRO. (2.4)

3 DOSAGE FORMS AND STRENGTHS

Transdermal System: 1 mg/24 hours, 2 mg/24 hours, 3 mg/24 hours, 4 mg/24 hours, 6 mg/24 hours, and 8 mg/24 hours of rotigotine. (3)

4 CONTRAINDICATIONS

History of hypersensitivity to rotigotine or components of the transdermal patch. (4)

5 WARNINGS AND PRECAUTIONS

- Contains sodium metabisulfite that may cause allergic-type reactions in those with sulfite sensitivity. (5.1)
- Falling asleep during activities of daily living, including the operation of motor vehicles, and somnolence may occur. (5.2)
- Hallucinations/psychosis and dyskinesia may occur. (5.3, 5.9)
- Symptomatic postural hypotension and syncope may occur, especially during dose escalation. (5.4, 5.5)
- Consider dose reduction or stopping NEUPRO if patient develops compulsive behaviors. (5.6)
- Elevation of blood pressure and heart rate may occur. (5.7)
- Application site reactions can occur and may be severe. (5.10)
- Hyperpyrexia and confusion may occur with sudden discontinuation or dose reduction. (5.14)

6 ADVERSE REACTIONS

- Parkinson's disease: Most common adverse reactions (at least 5% greater than placebo) were nausea, vomiting, somnolence, application site reactions, dizziness, anorexia, disturbances in initiating and maintaining sleep, hyperhidrosis, visual disturbance, peripheral edema, and dyskinesia. (6.1)
- Restless Legs Syndrome: Most common adverse reactions (at least 5% greater than placebo) were application site reactions, nausea, disturbances in initiating and maintaining sleep, somnolence, and headache. (6.1)

To report SUSPECTED ADVERSE REACTIONS, contact UCB, Inc. at 1-844-599-2273 or FDA at 1-800-FDA-1088 orwww.fda.gov/medwatch.

8 USE IN SPECIFIC POPULATIONS

Pregnancy: Based on animal data, may cause fetal harm. (8.1)

FULL PRESCRIBING INFORMATION

1 INDICATIONS AND USAGE

1.1 Parkinson's Disease (PD)

NEUPRO is indicated for the treatment of Parkinson's disease.

1.2 Restless Legs Syndrome (RLS)

NEUPRO is indicated for the treatment of moderate-to-severe primary Restless Legs Syndrome.

2 DOSAGE AND ADMINISTRATION

2.1 Dosage in Parkinson's Disease

Early-Stage Parkinson's Disease

In patients with early-stage Parkinson's disease, the recommended starting dose for NEUPRO is 2 mg/24 hours. Based upon individual patient clinical response and tolerability, NEUPRO dosage may be increased weekly by 2 mg/24 hours if additional therapeutic effect is needed. The lowest effective dose is 4 mg/24 hours. The maximum recommended dose for early-stage Parkinson's disease is 6 mg/24 hours.

Advanced-Stage Parkinson's Disease

In patients with advanced-stage Parkinson's disease, the recommended starting dose for NEUPRO is 4 mg/24 hours. Based upon individual patient clinical response and tolerability, NEUPRO dosage may be increased weekly by 2 mg/24 hours if additional therapeutic effect is needed. The maximum recommended dose for advanced-stage Parkinson's disease is 8 mg/24 hours.

2.2 Dosage in Restless Legs Syndrome

In patients with Restless Legs Syndrome, the recommended starting dose for NEUPRO is 1 mg/24 hours. Based upon individual patient clinical response and tolerability, NEUPRO dosage may be increased weekly by 1 mg/24 hours if additional therapeutic effect is needed. The lowest effective dose is 1 mg/24 hours. The maximum recommended dose is 3 mg/24 hours.

2.3 Administration Information

NEUPRO is applied once a day. The adhesive side of the transdermal system should be applied to clean, dry, intact healthy skin on the front of the abdomen, thigh, hip, flank, shoulder, or upper arm. The transdermal system should be applied at approximately the same time every day, at a convenient time for the patient.

Because NEUPRO is administered transdermally, food is not expected to affect absorption and it can be applied irrespective of the timing of meals. The application site for NEUPRO should be moved on a daily basis (for example, from the right side to the left side and from the upper body to the lower body). NEUPRO should not be applied to the same application site more than once every 14 days and should not be placed on skin that is oily, irritated, or damaged, or where it will be rubbed by tight clothing. If it is necessary to apply NEUPRO to a hairy area, the area should be shaved at least 3 days prior to NEUPRO application. The system should be applied immediately after opening the pouch and removing the protective liner. The system should be pressed firmly in place for 30 seconds, making sure there is good contact, especially around the edges. If the patient forgets to replace NEUPRO, or if the transdermal system becomes dislodged, another transdermal system should be applied for the remainder of the day. The prescribed dose may be achieved using single or multiple patches [see Patient Counseling Information (17)].

2.4 Discontinuation of NEUPRO

For discontinuation of NEUPRO in patients with Parkinson's disease, reduce the daily dose by a maximum of 2 mg every 24 hours preferably every other day, until complete withdrawal of NEUPRO is achieved.

For discontinuation of NEUPRO in patients with Restless Legs Syndrome, reduce the daily dose by 1 mg every 24 hours preferably every other day, until complete withdrawal of NEUPRO is achieved.

3 DOSAGE FORMS AND STRENGTHS

Transdermal System: 1 mg/24 hours, 2 mg/24 hours, 3 mg/24 hours, 4 mg/24 hours, 6 mg/24 hours, and 8 mg/24 hours of rotigotine.

4 CONTRAINDICATIONS

NEUPRO is contraindicated in patients who have demonstrated hypersensitivity to rotigotine or the components of the transdermal system.

5 WARNINGS AND PRECAUTIONS

5.1 Sulfite Sensitivity

NEUPRO contains sodium metabisulfite, a sulfite that may cause allergic-type reactions including anaphylactic symptoms and life-threatening or less severe asthmatic episodes in certain susceptible people. The overall prevalence of sulfite sensitivity in the general population is unknown. Sulfite sensitivity is seen more frequently in asthmatic than in nonasthmatic people.

5.2 Falling Asleep During Activities of Daily Living and Somnolence

Patients with early- and advanced-stage Parkinson's disease and with Restless Legs Syndrome treated with NEUPRO have reported falling asleep while engaged in activities of daily living, including the operation of motor vehicles, which sometimes resulted in accidents. Although many of these patients reported somnolence while on NEUPRO, some did not perceive warning signs, such as excessive drowsiness, and believed that they were alert immediately prior to the event. Some of these events have been reported as late as one year after initiation of treatment. In clinical trials in patients with Restless Legs Syndrome, 2% of patients treated with the maximum recommended NEUPRO dose (3 mg/24 hours) reported sleep attacks compared to 0% of placebo-treated patients.

It has been reported that falling asleep while engaged in activities of daily living always occurs in a setting of pre-existing somnolence, although patients may not give such a history. For this reason, prescribers should reassess patients for drowsiness or sleepiness especially since some of the events occur well after the start of treatment.

Somnolence is a common occurrence in patients receiving NEUPRO. In patients taking the maximum recommended NEUPRO dose, there was an increased risk of somnolence for early-stage Parkinson's disease (NEUPRO 19%, placebo 3%), for advanced-stage Parkinson's disease (NEUPRO 32%, placebo 28%), and for Restless Legs Syndrome (NEUPRO 10%, placebo 4%). Prescribers should also be aware that patients may not acknowledge drowsiness or sleepiness until directly questioned about drowsiness or sleepiness during specific activities. Patients should be advised to exercise caution while driving, operating machines, or working at heights during treatment with NEUPRO. Patients who have already experienced somnolence and/or an episode of sudden sleep onset should not participate in these activities while taking NEUPRO.

Before initiating treatment with NEUPRO, patients should be advised of the potential to develop drowsiness and specifically asked about factors that may increase this risk with NEUPRO such as concomitant sedating medications and the presence of sleep disorders. If a patient develops daytime sleepiness or episodes of falling asleep during activities that require active participation (e.g., conversations, eating, etc.), NEUPRO should ordinarily be discontinued [see Dosage and Administration (2.4)] .

If a decision is made to continue NEUPRO, patients should be advised not to drive and to avoid other potentially dangerous activities. There is insufficient information to establish whether dose reduction will eliminate episodes of falling asleep while engaged in activities of daily living.

5.3 Hallucinations/Psychosis

There was an increased risk for hallucinations in patients with advanced-stage Parkinson's disease treated with NEUPRO. In patients taking the maximum recommended NEUPRO dose, the incidence of hallucinations was 7% for NEUPRO and 3% for placebo, and this treatment difference increased with increasing dose.

Hallucinations were of sufficient severity to cause discontinuation of treatment (mainly during the dose escalation/titration period) in 3% of advanced-stage Parkinson's disease patients treated with the maximum recommended dose of NEUPRO compared with 1% of placebo-treated patients. Hallucinations have also been reported in post-marketing reports.

Post-marketing reports indicate that patients with Parkinson's disease or RLS may experience new or worsening mental status and behavioral changes, which may be severe, including psychotic behavior during NEUPRO treatment or after starting or increasing the dose of NEUPRO. Other drugs prescribed to improve the symptoms of Parkinson's disease or RLS can have similar effects on thinking and behavior. This abnormal thinking and behavior may consist of one or more of the following: paranoid ideation, delusions, hallucinations, confusion, symptoms of mania (e.g., insomnia, psychomotor agitation), disorientation, aggressive behavior, agitation, and delirium. These various manifestations of psychotic behavior were also observed during the clinical development of NEUPRO for early- and advanced-stage Parkinson's disease and Restless Legs Syndrome.

Patients with a major psychotic disorder should ordinarily not be treated with NEUPRO because of the risk of exacerbating psychosis. In addition, certain medications used to treat psychosis may exacerbate the symptoms of Parkinson's disease and may decrease the effectiveness of NEUPRO [see Drug Interactions (7.1)].

5.4 Symptomatic Hypotension

Dopaminergic agonists, in clinical studies and clinical experience, appear to impair the systemic regulation of blood pressure, resulting in postural/orthostatic hypotension, especially during dose escalation. Parkinson's disease patients, in addition, appear to have an impaired capacity to respond to a postural challenge. For these reasons, both Parkinson's and Restless Legs Syndrome patients being treated with dopaminergic agonists ordinarily (1) require careful monitoring for signs and symptoms of postural hypotension, especially during dose escalation, and (2) should be informed of this risk.

An increased risk for decreases in systolic and diastolic blood pressure were observed when supine, standing, and changing from supine to standing position in patients treated with NEUPRO. In patients taking the maximum recommended NEUPRO dose, orthostatic (change from supine to standing) decreases in systolic blood pressure (at least 20 mm Hg or greater) was 16% for NEUPRO and 14% for placebo in patients with early-stage Parkinson's disease, 32% for NEUPRO and 27% for placebo in patients with advanced-stage Parkinson's disease, and 13% for NEUPRO and 11% for placebo in patients with Restless Legs Syndrome.

More severe decreases in systolic blood pressure (40 mm Hg or greater) and in diastolic blood pressure (20 mm Hg or greater) also occurred more frequently (NEUPRO incidence at least 2% greater than placebo) in patients with early- and advanced-stage Parkinson's disease during measurements when supine, standing, or changing from supine to standing position. Patients experienced dose-related decreases in blood pressure at different times throughout the trial including the final visit.

An analysis using a variety of adverse reaction terms suggestive of orthostatic hypotension, including dizziness/postural dizziness and others, showed an increased risk for all patients treated with NEUPRO. For the maximum recommended NEUPRO dose, the incidence of adverse reactions suggestive of hypotension/orthostatic hypotension was 29% for NEUPRO and 11% for placebo in early-stage Parkinson's disease, 27% for NEUPRO and 23% for placebo in advanced-stage Parkinson's disease, and 8% for NEUPRO and 7% for placebo in Restless Legs Syndrome.

This increased risk for symptomatic hypotension and decreases in blood pressure was observed in a setting in which patients were very carefully titrated, and patients with clinically relevant cardiovascular disease or symptomatic orthostatic hypotension at baseline had been excluded from this study. The increased risk for significant decreases in blood pressure or orthostatic hypotension occurred especially in the dose escalation/titration period.

5.5 Syncope

Syncope has been reported in patients using dopamine agonists, and for this reason patients should be alerted to the possibility of syncope. Because the studies of NEUPRO excluded patients with clinically relevant cardiovascular disease, patients with severe cardiovascular disease should be asked about symptoms of syncope and pre-syncope.

5.6 Impulse Control/Compulsive Behaviors

Patients may experience intense urges to gamble, increased sexual urges, intense urges to spend money, binge eating, and/or other intense urges, and the inability to control these urges while taking one or more of the medications, including NEUPRO, that increase central dopaminergic tone. In some cases, although not all, these urges were reported to have stopped when the dose was reduced or the medication was discontinued. Because patients may not recognize these behaviors as abnormal, it is important for prescribers to specifically ask patients or their caregivers about the development of new or increased gambling urges, sexual urges, uncontrolled spending, or other urges while being treated with NEUPRO for Parkinson's disease or RLS. Dopamine dysregulation syndrome, the repeated use of more NEUPRO than as prescribed to manage their symptoms of Parkinson's disease or RLS, was observed in some patients during treatment with NEUPRO. Physicians should consider dose reduction or stopping the medication if a patient develops such urges while taking NEUPRO .

5.7 Elevation of Blood Pressure and Heart Rate

Some patients treated with NEUPRO exhibited increases in systolic blood pressure (greater than 180 mm Hg) and/or diastolic blood pressure (greater than 105 mm Hg) while supine or standing. In patients with advanced-stage Parkinson's disease, this increased risk for systolic blood pressure greater than 180 mm Hg was 5% for NEUPRO and 3% for placebo and for diastolic blood pressure greater than 105 mm Hg was 4% for NEUPRO and 0% for placebo. In patients with Restless Legs Syndrome, this increased risk for diastolic blood pressure greater than 105 mm Hg was 8% for NEUPRO and 4% for placebo.

Increases in systolic blood pressure (at least 20 mm Hg or more) and in diastolic blood pressure (at least 10 mm Hg or more) occurred more frequently (incidence at least 5% greater than placebo) in all patients (i.e., early- and advanced-stage Parkinson's disease and Restless Legs Syndrome) taking the maximum recommended NEUPRO dose. These increases in systolic and diastolic blood pressure were observed when supine, standing, and changing from supine to standing position. More severe increases in systolic blood pressure (40 mm Hg or more) and in diastolic blood pressure (20 mm Hg or more) also occurred more frequently (incidence at least 2% greater than placebo) in NEUPRO-treated patients with early- and advanced-stage Parkinson's disease and with Restless Legs Syndrome during measurements when supine, standing, and/or changing from supine to standing position.

In the placebo-controlled trials, there was an increased risk for hypertension as an adverse reaction with the maximum recommended NEUPRO dose in patients with advanced-stage Parkinson's disease (NEUPRO 3% vs. placebo 0%) and Restless Legs Syndrome (NEUPRO 4% vs. placebo 0%).

Some patients treated with NEUPRO exhibited increased pulse (greater than 100 beats per minute) while supine and/or standing. In patients with advanced-stage Parkinson's disease, there was an increased risk (at least 2% greater than placebo) of increased pulse for patients taking the maximum recommended NEUPRO dose. In patients with Restless Legs Syndrome, there was an increased risk (at least 5% greater than placebo) of increased pulse for patients taking the maximum recommended NEUPRO dose.

These findings of blood pressure and heart rate elevations should be considered when treating patients with cardiovascular disease.

5.8 Weight Gain and Fluid Retention

Patients taking the maximum recommended NEUPRO dose for early-stage Parkinson's disease had a higher incidence (2%) of substantial weight gain (more than 10% of baseline weight) than patients taking placebo (0%). In advanced-stage Parkinson's disease, the incidence of weight gain more than 10% of baseline weight was 9% in NEUPRO-treated patients (for the maximum recommended dose) and 1% in placebo-treated patients. This weight gain was frequently associated with the development of peripheral edema in patients with Parkinson's disease, suggesting that NEUPRO may cause fluid retention in some Parkinson's patients. In patients taking the maximum recommended NEUPRO dose, the incidence of peripheral edema was 3% for NEUPRO and 2% for placebo in early-stage Parkinson's disease and 9% for NEUPRO and 1% for placebo in advanced-stage Parkinson's disease. These treatment differences increased further with treatment at NEUPRO dosing above the maximum recommended doses. Monitor for weight gain and fluid retention when treating patients with concomitant illnesses such as congestive heart failure or renal insufficiency.

5.9 Dyskinesia

NEUPRO may potentiate the dopaminergic side effects of levodopa and may cause or exacerbate pre-existing dyskinesia. For the maximum recommended NEUPRO dose, the incidence of dyskinesia was increased for NEUPRO (NEUPRO 14% vs. placebo 7%) in patients with advanced-stage Parkinson's disease, and this incidence increased with increasing dose. Patients treated with the maximum recommended dose of NEUPRO also had an increased risk (NEUPRO 3% vs. placebo 0%) for early discontinuation from the study because of dyskinesia.

5.10 Application Site Reactions

Application site reactions (ASRs) occurred at a greater frequency in the NEUPRO-treated patients than in placebo-treated patients in the double-blind, placebo-controlled, dose-response studies with NEUPRO. For the maximum recommended NEUPRO dose, the incidence of application site reactions was 32% for NEUPRO and 19% for placebo in patients with early-stage Parkinson's disease, 36% for NEUPRO and 13% for placebo in patients with advanced-stage Parkinson's disease, and 43% for NEUPRO and 4% for placebo in patients with Restless Legs Syndrome. ASRs exhibited a dose-dependent relationship for all doses for patients with early- and advanced-stage Parkinson's disease and Restless Legs Syndrome. ASRs were also of sufficient severity to cause study discontinuation for patients with early-stage Parkinson's disease (NEUPRO 3% vs. placebo 0%), advanced-stage Parkinson's disease (NEUPRO 2% vs. placebo 0%), and Restless Legs Syndrome (NEUPRO 12% vs. placebo 0%) who were treated with the maximum recommended NEUPRO dose.

The signs and symptoms of these reactions generally were localized erythema, edema, or pruritus limited to the patch area and usually did not lead to dose reduction. Generalized skin reactions (e.g., allergic rash, including erythematous, macular-papular rash, or pruritus) have been reported at lower rates than ASRs during the development of NEUPRO.

In a clinical study designed to investigate the cumulative skin irritation of NEUPRO, daily rotation of NEUPRO application sites has been shown to reduce the incidence of ASRs in comparison to repetitive application to the same site. In a clinical study investigating the skin sensitizing potential of NEUPRO in 221 healthy subjects, no case of contact sensitization was observed. Localized sensitization reactions were observed in a study with healthy subjects by continuously rotating a 0.5 mg/24 hours transdermal system, after induction of maximal irritational stress was achieved by repetitive transdermal system application to the same site.

If a patient reports a persistent application site reaction (of more than a few days), reports an increase in severity, or reports a skin reaction spreading outside the application site, an assessment of the risk and benefits for the individual patient should be conducted. If a generalized skin reaction associated with the use of NEUPRO is observed, NEUPRO should be discontinued.

5.11 Augmentation and Rebound in RLS

Augmentation is a worsening of RLS symptoms during treatment, leading to an increase in overall symptom severity or earlier time of symptom onset each day compared to before initiation of treatment. Use of dopaminergic medications, including NEUPRO, may result in augmentation.

Rebound, an exacerbation of RLS symptoms, is considered to be an end of dose effect, related to the half-life of the therapeutic agent. Reports in the published literature indicate discontinuation or wearing off of dopaminergic medications can result in rebound.

5.12 Magnetic Resonance Imaging and Cardioversion

The backing layer of NEUPRO contains aluminum. To avoid skin burns, NEUPRO should be removed prior to magnetic resonance imaging or cardioversion.

5.13 Heat Application

The effect of application of heat to the transdermal system has not been studied. However, heat application has been shown to increase absorption several fold with other transdermal products. Patients should be advised to avoid exposing the NEUPRO application site to external sources of direct heat, such as heating pads or electric blankets, heat lamps, saunas, hot tubs, heated water beds, and prolonged direct sunlight.

5.14 Hyperpyrexia and Confusion

A symptom complex resembling the neuroleptic malignant syndrome (characterized by elevated temperature, muscular rigidity, altered consciousness, rhabdomyolysis, and/or autonomic instability), with no other obvious etiology, has been reported in association with rapid dose reduction, withdrawal of, or changes in anti- Parkinsonian therapy. Therefore, it is recommended that the dose be tapered at the end of NEUPRO treatment [see Dosage and Administration (2.4)].

5.15 Withdrawal Symptoms

Symptoms including apathy, anxiety, depression, fatigue, insomnia, sweating and pain have been reported during taper or after discontinuation of dopamine agonists, including NEUPRO. These symptoms generally do not respond to levodopa.

Prior to discontinuation, patients should be informed about potential withdrawal symptoms, and monitored during and after discontinuation. In case of severe withdrawal symptoms, a trial re-administration of a dopamine agonist at the lowest effective dose may be considered.

5.16 Fibrotic Complications

Cases of retroperitoneal fibrosis, pulmonary infiltrates, pleural effusion, pleural thickening, pericarditis, and cardiac valvulopathy have been reported in some patients treated with ergot-derived dopaminergic agents. While these complications may resolve when the drug is discontinued, complete resolution does not always occur.

Although these adverse events are believed to be related to the ergoline structure of these compounds, whether other, nonergot-derived dopamine agonists can cause them is unknown.

5.17 Binding to Melanin

As has been reported with other dopamine agonists, binding to melanin-containing tissues (i.e., eyes) in the pigmented rat and monkey was evident after a single dose of rotigotine, but was slowly cleared over the 14-day observation period.

6 ADVERSE REACTIONS

The following serious adverse reactions are discussed below and elsewhere in the labeling:

- Sulfite Sensitivity [see Warnings and Precautions (5.1)]
- Falling Asleep During Activities of Daily Living and Somnolence [see Warnings and Precautions (5.2)]
- Hallucinations/Psychosis [see Warnings and Precautions (5.3)]
- Symptomatic Hypotension [see Warnings and Precautions (5.4)]
- Syncope [see Warnings and Precautions (5.5)]
- Impulse Control/Compulsive Behaviors [see Warnings and Precautions (5.6)]
- Elevation of Blood Pressure and Heart Rate [see Warnings and Precautions (5.7)]
- Weight Gain and Fluid Retention [see Warnings and Precautions (5.8)]
- Dyskinesia [see Warnings and Precautions (5.9)]
- Application Site Reactions [see Warnings and Precautions (5.10)]
- Augmentation and Rebound in RLS [see Warnings and Precautions (5.11)]
- Hyperpyrexia and Confusion [see Warnings and Precautions (5.14)]
- Withdrawal Symptoms [see Warnings and Precautions (5.15)]
- Fibrotic Complications [see Warnings and Precautions (5.16)]

6.1 Clinical Trials Experience

Because clinical trials are conducted under widely varying conditions, the incidence of adverse reactions (number of unique patients experiencing an adverse reaction associated with treatment/total number of patients treated) observed in the clinical trials of a drug cannot be directly compared to incidence of adverse reactions in the clinical trials of another drug and may not reflect the incidence of adverse reactions observed in practice.

Adverse Reactions in Early-Stage Parkinson's Disease

The safety of NEUPRO was evaluated in a total of 649 early-stage Parkinson's disease patients who participated in three double-blind, placebo-controlled studies with durations of 3 to 9 months. Additional safety information was collected in short-term studies and two open-label extension studies in patients with early-stage Parkinson's disease.

In the double-blind, placebo-controlled, dose-response study in patients with early-stage Parkinson's disease, the most common adverse reactions (at least 5% greater than placebo) for the maximum recommended dose of NEUPRO (6 mg/24 hours) were nausea, vomiting, somnolence, application site reactions, dizziness, anorexia, disturbances in initiating and maintaining sleep, hyperhidrosis, and visual disturbance.

In this trial, 12% of patients treated with the maximum recommended NEUPRO dose (6 mg/24 hours) discontinued treatment because of adverse reactions, compared with 6% of patients who received placebo.

Table 1 summarizes the adverse reactions that occurred in greater than 2% of NEUPRO-treated patients and more frequent than in placebo-treated patients in a double-blind, placebo-controlled, fixed-dose trial in patients with early-stage Parkinson's disease. Incidences for the non-recommended 8 mg/24 hours dose are also shown.

Table 1 Adverse Reactions in a Placebo-Controlled, Fixed-Dose Trial in Patients with Early-Stage Parkinson's Disease
Adverse Reaction | Placebo N=64 % | NEUPRO Dose
Adverse Reaction | Placebo N=64 % | 2 mg/24h N=67 % | 4 mg/24h N=63 % | 6 mg/24h N=65 % | 8 mg/24h N=70 %
Nausea | 13 | 34 | 38 | 48 | 41
Vomiting | 3 | 10 | 16 | 20 | 11
Somnolence | 3 | 12 | 14 | 19 | 20
Application and instillation site reactions | 19 | 21 | 19 | 32 | 43
Dizziness | 11 | 21 | 14 | 22 | 20
Anorexia | 0 | 2 | 2 | 9 | 4
Disturbances in initiating and maintaining sleep | 6 | 6 | 11 | 14 | 11
Hyperhidrosis | 3 | 3 | 3 | 11 | 3
Visual disturbance | 0 | 0 | 0 | 5 | 3
Abnormal dreams | 0 | 2 | 5 | 3 | 7
Abnormal Electrocardiogram T wave | 0 | 0 | 2 | 3 | 0
Balance disorder | 0 | 0 | 2 | 3 | 0
Dyspepsia | 0 | 2 | 2 | 3 | 0
Fatigue | 3 | 8 | 18 | 6 | 13
Tinnitus | 0 | 0 | 2 | 3 | 0
Constipation | 3 | 2 | 3 | 5 | 6
Erythema | 3 | 3 | 6 | 5 | 6
Hallucinations | 2 | 0 | 2 | 3 | 3
Muscle spasms | 2 | 3 | 2 | 3 | 4
Paresthesia | 2 | 3 | 3 | 3 | 0
Peripheral edema | 2 | 2 | 3 | 3 | 4
White blood cells urine positive | 2 | 3 | 3 | 3 | 1

The incidence of certain adverse reactions with NEUPRO was notably increased compared to placebo treatment (i.e., at least 5% greater than placebo) in either the titration or maintenance phases of the dose-response trial.

During the titration phase, this increased incidence of a treatment difference was observed for nausea, somnolence, vomiting, application site reactions (ASRs), dizziness, sweating increased, anorexia, and visual disturbance. During the maintenance phase, an increased incidence was observed for nausea and ASRs. Some adverse reactions developing in the titration phase persisted (at least 7 days) into the maintenance phase. These "persistent" adverse reactions included ASRs, anorexia, somnolence, and nausea.

Adverse Reactions in Advanced-Stage Parkinson's Disease

The safety evaluation of NEUPRO was based on a total of 672 NEUPRO-treated patients with advanced-stage Parkinson's disease who participated in three double-blind, placebo-controlled studies (two fixed-dose trials and one flexible-dose trial) with durations of 3 to 7 months. Patients received concomitant levodopa in these studies. Additional safety information was collected in earlier short-term studies and two open-label extension studies in patients with advanced-stage Parkinson's disease.

In the dose-response, placebo-controlled trial for advanced-stage Parkinson's disease, the most common adverse reactions (at least 5% greater than placebo) for the maximum recommended dose of NEUPRO (8 mg/24 hours) were application site reactions, nausea, peripheral edema, dizziness, and dyskinesia.

In this trial, approximately 15% of patients treated with the maximum recommended NEUPRO dose (8 mg/24 hours) discontinued treatment because of adverse reactions, compared with 9% of patients who received placebo.

Table 2 summarizes the adverse reactions that occurred in greater than 2% of NEUPRO-treated patients and more frequent than in placebo-treated patients in a double-blind, placebo-controlled, fixed-dose trial in patients with advanced-stage Parkinson's disease. Incidences for the non-recommended 12 mg/24 hours dose are also shown.

Table 2 Adverse Reactions in a Placebo-Controlled, Fixed-Dose Trial in Patients with Advanced-Stage Parkinson's Disease
Adverse Reaction | Placebo N=120 % | NEUPRO Dose
Adverse Reaction | Placebo N=120 % | 8 mg/24h N=118 % | 12 mg/24h N=111 %
Application and instillation site reactions | 13 | 36 | 46
Nausea | 19 | 28 | 22
Peripheral edema | 1 | 9 | 14
Dizziness | 15 | 23 | 14
Dyskinesia | 7 | 14 | 17
Somnolence | 28 | 32 | 32
Vomiting | 6 | 10 | 8
Arthralgia | 7 | 11 | 8
Hallucinations | 3 | 7 | 13
Hyperhidrosis | 0 | 3 | 1
Sinus congestion | 0 | 3 | 2
Constipation | 6 | 9 | 5
Disturbances in initiating and maintaining sleep | 6 | 9 | 14
First degree atrioventricular block | 0 | 3 | 0
Herpes simplex | 0 | 3 | 0
Hypertension | 0 | 3 | 5
Influenza | 0 | 3 | 1
Nasal congestion | 0 | 3 | 3
Headache | 8 | 10 | 8
Diarrhea | 5 | 7 | 5
Basal cell carcinoma | 1 | 3 | 0
Cough | 1 | 3 | 3
Dyspepsia | 2 | 3 | 0
Erythema | 1 | 3 | 2
Hot flush | 1 | 3 | 0
Paresthesias | 3 | 4 | 3
Tremor | 3 | 4 | 3
Hypoaesthesia | 2 | 3 | 3
Nightmare | 2 | 3 | 5

The incidence of certain adverse reactions with NEUPRO was notably increased compared to placebo treatment (i.e., at least 5% greater than placebo) in either the titration or maintenance phases of the dose-response trial.

During the titration phase, an increased incidence was observed for application site reactions (ASRs), nausea, hallucinations, constipation, dyskinesia, and dizziness. During the maintenance phase, an increased incidence was observed for ASRs and peripheral edema. Some adverse reactions developing in the titration phase persisted (at least 7 days) into the maintenance phase. A notably "persistent" adverse reaction was ASRs.

Adverse Reactions in Restless Legs Syndrome

The safety evaluation of NEUPRO was based on 745 NEUPRO-treated patients with Restless Legs Syndrome who participated in two double-blind, placebo-controlled studies with maintenance durations of 6 months.

Additional safety information was collected in earlier short-term studies and three open-label extension studies in patients with RLS.

In the two double-blind, placebo-controlled, fixed-dose trials for RLS, the most common adverse reactions (at least 5% greater than placebo) for the maximum recommended dose of NEUPRO (3 mg/24 hours) were application site reactions, nausea, disturbances in initiating and maintaining sleep, somnolence, and headache.

In the two fixed-dose, placebo-controlled trials, 24% of patients treated with the maximum recommended NEUPRO dose (3 mg/24 hours) discontinued treatment because of adverse reactions, compared with 3% of patients who received placebo.

Table 3 summarizes the adverse reactions that occurred in at least 2% of NEUPRO-treated patients and more frequent than in placebo-treated patients in two double-blind, placebo-controlled, fixed-dose trials in patients with Restless Legs Syndrome.

Table 3 Adverse Reactions in Pooled Placebo-Controlled, Fixed-Dose Trials of Patients with Restless Legs Syndrome
Adverse Reaction | Placebo N=217 % | NEUPRO Dose
Adverse Reaction | Placebo N=217 % | 0.5 mg/24h N=99 % | 1 mg/24h N=215 % | 2 mg/24h N=211 % | 3 mg/24h N=220 %
Application and instillation site reactions | 4 | 23 | 27 | 38 | 43
Nausea | 10 | 18 | 15 | 23 | 21
Disturbances in initiating and maintaining sleep | 3 | 2 | 4 | 3 | 10
Headache | 11 | 21 | 15 | 18 | 16
Asthenic conditions [Asthenic conditions is a high-level term for the following preferred terms: asthenia, malaise, and fatigue.] | 8 | 11 | 7 | 14 | 12
Somnolence | 4 | 8 | 5 | 8 | 10
Hypertension | 0 | 3 | 1 | 1 | 4
Pruritus | 3 | 9 | 4 | 3 | 7
Dry mouth | 4 | 3 | 3 | 3 | 7
Vomiting | 1 | 2 | 2 | 4 | 4
Dizziness | 6 | 7 | 5 | 9 | 6
Hyperhidrosis | 2 | 1 | 3 | 5 | 3
Abnormal dreams | 0 | 2 | 1 | 2 | 3
Irritability | 0 | 0 | 1 | 3 | 1
Muscle spasms | 1 | 3 | 1 | 4 | 1
Dyspepsia | 1 | 2 | 1 | 2 | 3
Hot flush | 1 | 4 | 1 | 3 | 0
Menstrual disorder | 0 | 0 | 0 | 2 | 1
Sleep disorder | 1 | 0 | 2 | 3 | 3
Viral gastroenteritis | 0 | 1 | 1 | 2 | 1
Sleep attacks | 0 | 0 | 1 | 0 | 2
Sexual desire disorder | 3 | 6 | 4 | 4 | 5
Depression | 1 | 3 | 1 | 2 | 1
Decreased serum ferritin | 1 | 2 | 1 | 1 | 2
Vertigo | 1 | 0 | 4 | 3 | 1
Constipation | 3 | 6 | 3 | 2 | 5
Erythema | 1 | 1 | 1 | 0 | 2
Sinusitis | 1 | 2 | 1 | 2 | 3
Diarrhea | 4 | 6 | 4 | 5 | 4
Increased weight | 1 | 3 | 1 | 1 | 2
Nasopharyngitis | 7 | 5 | 10 | 7 | 8

The incidence of certain adverse reactions with NEUPRO treatment was increased compared to placebo (i.e., at least 5% greater than placebo) in either the titration or maintenance phases of the dose-response trials. During the titration phase, an increased incidence was observed for application site reactions (ASRs), nausea, headache, asthenic conditions, and disturbances in initiating and maintaining sleep. During the maintenance phase, an increased incidence was observed for ASRs. Some adverse reactions developing in the titration phase persisted (at least 7 days) into the maintenance phase. These "persistent" adverse reactions were ASRs, nausea, and disturbances in initiating and maintaining sleep.

6.2 Laboratory Changes

Some clinical laboratory analytes were abnormal in patients treated with the maximum recommended NEUPRO dose in the fixed-dose, placebo-controlled, dose-response trials for patients with early- and advanced-stage Parkinson's disease and with RLS.

Patients with early-stage Parkinson's disease receiving NEUPRO had an increased risk for low hemoglobin below the normal reference range (NEUPRO 8% vs. placebo 2%) and for decreased hematocrit below the normal reference range (NEUPRO 8% vs. placebo 5%). Patients with advanced-stage Parkinson's disease receiving NEUPRO had an increased risk for a low hemoglobin below the normal reference range (NEUPRO 15% vs. placebo 11%) and for decreased hematocrit below the normal reference range (NEUPRO 17% vs. placebo 14%). Patients with RLS receiving NEUPRO had an increased risk for a decreased hemoglobin below the normal reference range (NEUPRO 15% vs. placebo 12%). There was also an increased risk for markedly decreased hemoglobin and hematocrit (NEUPRO 2% vs. placebo 0%) in patients with advanced-stage Parkinson's disease receiving NEUPRO and for markedly decreased hematocrit (NEUPRO 1% vs. placebo 0%) in patients with RLS receiving NEUPRO.

Patients with early-stage Parkinson's disease receiving NEUPRO had an increased risk for elevated serum blood urea nitrogen (BUN) above the normal reference range (NEUPRO 11% vs. placebo 2%). There was also an increased risk for markedly elevated serum BUN (NEUPRO 3% vs. placebo 2%) in patients with advanced-stage Parkinson's disease receiving NEUPRO.

There was an increased risk for low serum glucose below the normal reference range in patients with early- stage Parkinson's disease receiving NEUPRO (NEUPRO 15% vs. placebo 6%) and in patients with advanced-stage Parkinson's disease (NEUPRO 10% vs. placebo 7%). There was also an increased risk for markedly decreased serum glucose (NEUPRO 1% vs. placebo 0%) in patients with advanced-stage Parkinson's disease receiving NEUPRO.

Serum creatine phosphokinase (CPK) was elevated in Japanese patients taking NEUPRO for early- or advanced-stage Parkinson's disease in placebo-controlled, flexible-dose studies conducted in Japan. The frequency of CPK elevation observed in patients receiving NEUPRO for early-stage Parkinson's disease was 40% (35/88) in the NEUPRO group compared to 17% (15/89) in the placebo group. The frequency of CPK elevation observed in patients receiving NEUPRO for advanced-stage Parkinson's disease was 39% (99/253) in the NEUPRO group compared to 20% (34/171) in the placebo group using pooled data from two studies.

Increased CPK occurred at any time during the respective studies, and in some instances increased CPK was observed at two or more consecutive visits. The total daily dose of NEUPRO taken by patients with early- and advanced-stage Parkinson's disease ranged between 2 mg/24 hours to 16 mg/24 hours. Studies of NEUPRO conducted outside of Japan did not include assessments of serum CPK in patients treated for Parkinson's disease .Increased CPK was also reported in postmarketing data.

6.3 Postmarketing Experience

The following adverse reaction has been identified during post-approval use of NEUPRO. Because these reactions are reported voluntarily from a population of uncertain size, it is not always possible to reliably estimate their frequency or establish a causal relationship to drug exposure.

General Disorders and Administration Site Conditions: withdrawal symptoms [see Warnings and Precautions (5.15)]

Nervous System Disorders: Dropped head syndrome

Musculoskeletal and connective tissue disorders:Rhabdomyolysis

7 DRUG INTERACTIONS

7.1 Dopamine Antagonists

Dopamine antagonists, such as antipsychotics or metoclopramide, may diminish the effectiveness of NEUPRO [see Clinical Pharmacology (12.3)] .

8 USE IN SPECIFIC POPULATIONS

8.1 Pregnancy

Risk Summary

There are no adequate data on the developmental risk associated with the use of NEUPRO in pregnant women. In animal studies, rotigotine was shown to have adverse effects on embryofetal development when administered during pregnancy at doses similar to or lower than those used clinically [ see Data].

In the U.S. general population, the estimated background risk of major birth defects and of miscarriage in clinically recognized pregnancies is 2% to 4% and 15% to 20%, respectively. The background risk of major birth defects and miscarriage in the indicated population is unknown.

Data

Animal Data

Rotigotine administered subcutaneously (0, 10, 30, or 90 mg/kg/day) to pregnant mice during organogenesis (gestation days 6 through 15) resulted in increased incidences of delayed skeletal ossification and decreased fetal body weights at the two highest doses and an increase in embryofetal death at the high dose. The no-effect dose for embryofetal developmental toxicity in mice is approximately 6 times the maximum recommended human dose (MRHD) for Parkinson's disease (8 mg/24 hours) on a body surface area (mg/m^2) basis. Rotigotine administered subcutaneously (0, 0.5, 1.5, or 5 mg/kg/day) to pregnant rats during organogenesis (gestation days 6 through 17) resulted in increased embryofetal death at all doses. The lowest effect dose is less than the MRHD on a mg/m^2basis. This effect in rats is thought to be due to the prolactin-lowering effect of rotigotine. When rotigotine was administered subcutaneously (0, 5, 10, or 30 mg/kg/day) to pregnant rabbits during organogenesis (gestation days 7 through 19), an increase in embryofetal death occurred at the two highest doses tested. The no-effect dose is 12 times the MRHD on a mg/m^2basis.

In a study in which rotigotine was administered subcutaneously (0, 0.1, 0.3, or 1 mg/kg/day) to rats throughout pregnancy and lactation (gestation day 6 through postnatal day 21), impaired growth and development during lactation and long-term neurobehavioral abnormalities were observed in the offspring at the highest dose tested; when those offspring were mated, growth and survival of the next generation were adversely affected. The no- effect dose for pre- and postnatal developmental toxicity (0.3 mg/kg/day) is less than the MRHD on a mg/m^2basis.

8.2 Lactation

Risk Summary

There are no data on the presence of rotigotine in human milk, the effects of rotigotine on the breastfed infant, or the effects of rotigotine on milk production. However, inhibition of lactation may occur because rotigotine decreases secretion of prolactin in humans. Studies have shown that rotigotine and/or its metabolite(s) are excreted in rat milk.

The developmental and health benefits of breastfeeding should be considered along with the mother's clinical need for NEUPRO and any potential adverse effects on the breastfed infant from NEUPRO or from the underlying maternal condition.

8.4 Pediatric Use

Safety and effectiveness in pediatric patients for any indication have not been established.

8.5 Geriatric Use

Of patients receiving NEUPRO in clinical studies for the treatment of Parkinson's disease, approximately 50% were age 65 and over, and approximately 11% were age 75 and over. Among patients receiving NEUPRO in clinical studies for the treatment of RLS, 26% were age 65 and over. No overall differences in safety or effectiveness were observed between these patients and younger patients, and other reported clinical experience has not identified differences in responses between the elderly and younger patients, but greater sensitivity of some older individuals cannot be ruled out.

No overall differences in plasma levels of rotigotine were observed between patients who were 65 to 80 years old compared with younger patients receiving the same rotigotine doses.

10 OVERDOSAGE

10.1 Overdose Symptoms

The most likely symptoms of overdose would be those related to the pharmacodynamic profile of a dopamine agonist, including nausea, vomiting, hypotension, involuntary movements, hallucinations, confusion, convulsions, and other signs of excessive dopaminergic stimulation.

10.2 Overdose Management

There is no known antidote for overdosage of dopamine agonists. In case of suspected overdose, the excess transdermal system(s) should immediately be removed from the patient. Concentrations of rotigotine decrease after patch removal. The terminal half-life of rotigotine is 5 to 7 hours. The pharmacokinetic profile showed a biphasic elimination with an initial half-life of 3 hours. The patient's heart rate, heart rhythm, and blood pressure should be monitored. As shown in a study of renally impaired patients, dialysis is not expected to be beneficial. Treatment of overdose may require general supportive measures to maintain vital signs. If it is necessary to discontinue use of rotigotine after overdose, it should be discontinued gradually to prevent hyperpyrexia and confusion [see Dosage and Administration (2.4)and Warnings and Precautions (5.14)].

11 DESCRIPTION

NEUPRO is a transdermal system that provides continuous delivery of rotigotine, a non-ergoline dopamine agonist, for 24 hours following application to intact skin.

NEUPRO is available in six strengths as shown in Table 4.

Table 4 Nominal Dose, Drug Content, and Transdermal System Size
NEUPRO Nominal Dose | Rotigotine Content per System | NEUPRO System Size
1 mg/24 hours | 2.25 mg | 5 cm^2
2 mg/24 hours | 4.5 mg | 10 cm^2
3 mg/24 hours | 6.75 mg | 15 cm^2
4 mg/24 hours | 9 mg | 20 cm^2
6 mg/24 hours | 13.5 mg | 30 cm^2
8 mg/24 hours | 18 mg | 40 cm^2

The chemical name of rotigotine is (6S)-6-{propyl[2-(2-thienyl)ethyl]amino}-5,6,7,8-tetrahydro-1-naphthalenol. The empirical formula is C19H25NOS. The molecular weight is 315.48. The structural formula for rotigotine is:

The asterisk designates the chiral center.

System Components and Structure

NEUPRO is a thin, matrix-type transdermal system composed of three layers as shown in Figure 1:

Backing film
Drug matrix
Protective liner

Figure 1: System Schematic

1. A flexible, tan-colored backing film, consisting of an aluminized polyester film coated with a pigment-layer on the outer side. The backing provides structural support and protection of the drug-loaded adhesive layer from the environment.
2. A self-adhesive drug matrix layer, consisting of the active component rotigotine and the following inactive components: ascorbyl palmitate, povidone, silicone adhesive, sodium metabisulfite, and dl-alpha-tocopherol.
3. A protective liner, consisting of a transparent fluoropolymer-coated polyester film. This liner protects the adhesive layer during storage and is removed just prior to application.

12 CLINICAL PHARMACOLOGY

12.1 Mechanism of Action

Rotigotine is a non-ergoline dopamine agonist. The precise mechanism of action of rotigotine as a treatment for Parkinson's disease is unknown, although it is thought to be related to its ability to stimulate dopamine receptors within the caudate-putamen in the brain. The precise mechanism of action of rotigotine as a treatment for Restless Legs Syndrome is unknown but is thought to be related to its ability to stimulate dopamine receptors.

12.2 Pharmacodynamics

Cardiac Electrophysiology

There is no indication of a QT/QTc prolonging effect of NEUPRO in doses up to 24 mg/24 hours. The effects of NEUPRO at doses up to 24 mg/24 hours (supratherapeutic doses) on the QT/QTc interval was evaluated in a double-blind, randomized, placebo- and positive-controlled (moxifloxacin 400 mg IV, single dose), parallel-group trial with an overall treatment period of 52 days in male and female patients with advanced-stage Parkinson's disease. Assay sensitivity was confirmed by significant QTc prolongation by moxifloxacin.

12.3 Pharmacokinetics

On average, approximately 45% of the rotigotine from the patch is released within 24 hours (0.2 mg/cm^2). Rotigotine is primarily eliminated in the urine as inactive conjugates. After removal of the patch, plasma levels decreased with a terminal half-life of 5 to 7 hours. The pharmacokinetic profile showed a biphasic elimination with an initial half-life of 3 hours.

Absorption and Bioavailability

When single doses of 8 mg/24 hours are applied to the trunk, there is an average lag time of approximately 3 hours until drug is detected in plasma (range 1 to 8 hours). Tmaxtypically occurs between 15 to 18 hours post dose but can occur from 4 to 27 hours post dose. However, there is no characteristic peak concentration observed. Rotigotine displays dose-proportionality over a daily dose range of 1 mg/24 hours to 24 mg/24 hours. In the clinical studies of rotigotine effectiveness, the transdermal system application site was rotated from day to day (abdomen, thigh, hip, flank, shoulder, or upper arm) and the mean measured plasma concentrations of rotigotine were stable over the 6 months of maintenance treatment. Relative bioavailability for the different application sites at steady-state was evaluated in subjects with Parkinson's disease. In a single trial conducted in patients with early-stage Parkinson's disease, differences in bioavailability ranged from less than 1% (abdomen vs. hip) to 46% (shoulder vs. thigh) with shoulder application showing higher bioavailability.

Because rotigotine is administered transdermally, food should not affect absorption.

In a 14-day clinical study with rotigotine administered to healthy subjects, steady-state plasma concentrations were achieved within 2 to 3 days of daily dosing.

Average NEUPRO plasma concentrations (±95% CI) in patients with early-stage Parkinson's disease are shown in Figure 2 after application of a 8 mg/24 hours transdermal system to 1 of 6 application sites (shoulder, upper arm, flank, hip, abdomen, or thigh) on 2 different days during the maintenance phase.

Figure 2 Average NEUPRO Plasma Concentrations in Patients with Early-Stage Parkinson's Disease

Distribution

The weight normalized apparent volume of distribution (Vd/F) in humans is approximately 84 L/kg after repeated dose administration.

The binding of rotigotine to human plasma proteins is approximately 92% in vitroand 89.5% in vivo.

Metabolism and Elimination

Rotigotine is extensively metabolized by conjugation and N-dealkylation. After intravenous dosing the predominant metabolites in human plasma are sulfate conjugates of rotigotine, glucuronide conjugates of rotigotine, sulfate conjugates of the N-despropyl-rotigotine and conjugates of N-desthienylethyl-rotigotine. Multiple CYP isoenzymes, sulfotransferases and two UDP-glucuronosyltransferases catalyze the metabolism of rotigotine.

After removal of the patch, plasma levels decreased with a terminal half-life of 5 to 7 hours. The pharmacokinetic profile showed a biphasic elimination with an initial half-life of 3 hours.

Rotigotine is primarily excreted in urine (approximately 71%) as inactive conjugates of the parent compound and N-desalkyl metabolites. A smaller proportion is excreted in feces (approximately 23%). The major metabolites found in urine were rotigotine sulfate (16% to 22% of the absorbed dose), rotigotine glucuronide (11% to 15%), and N-despropyl-rotigotine sulfate metabolite (14% to 20%) and N-desthienylethyl-rotigotine sulfate metabolite (10% to 21%). Approximately 11% is renally eliminated as other metabolites. A small amount of unconjugated rotigotine is renally eliminated (less than 1% of the absorbed dose).

Drug Interaction Studies

CYP Interactions

In vitrostudies indicate that multiple CYP-isoforms are capable of catalyzing the metabolism of rotigotine. In human liver microsomes, no extensive inhibition of the metabolism of rotigotine was observed when co-incubated with CYP isoform specific inhibitors. If an individual CYP isoform is inhibited, other isoforms can catalyze rotigotine metabolism.

Rotigotine, the 5-O-glucuronide and its desalkyl and monohydroxy metabolites were analyzed for interactions with the human CYP isoenzymes CYP1A2, CYP2C9, CYP2C19, CYP2D6, and CYP3A4 in vitro. Based on these results, no risk for inhibition of CYP1A2, CYP2C9, and CYP3A4 catalyzed metabolism of other drugs is predicted at therapeutic rotigotine concentrations. There is a low risk of inhibition of CYP2C19 and CYP2D6 catalyzed metabolism of other drugs at therapeutic concentrations.

In human hepatocytes in vitro, there was no indication for induction of CYP1A2, CYP2B6, CYP2C9, CYP2C19, and CYP3A4.

Rotigotine is metabolized by multiple sulfotransferases and two UDP-glucuronosyltransferases (UGT1A9 and UGT2B15). These multiple pathways make it unlikely that inhibition of any one pathway would alter rotigotine concentrations significantly.

Protein Displacement, Warfarin

In vitro, no potential for displacement of warfarin by rotigotine (and vice versa) from their respective human serum albumin binding sites was detected.

Digoxin

The effect of rotigotine on the pharmacokinetics of digoxin has been investigated in vitroin Caco-2 cells. Rotigotine did not influence the P-glycoprotein-mediated transport of digoxin. Therefore, rotigotine would not be expected to affect the pharmacokinetics of digoxin.

Cimetidine

Co-administration of rotigotine (up to 4 mg/24 hours) with cimetidine (400 mg twice daily), an inhibitor of CYP1A2, CYP2C19, CYP2D6, and CYP3A4, did not alter the steady-state pharmacokinetics of rotigotine in healthy subjects.

Levodopa/Carbidopa

Co-administration of levodopa/carbidopa (100/25 mg twice daily) with rotigotine (4 mg/24 hours) had no effect on the steady-state pharmacokinetics of rotigotine; rotigotine had no effect on the pharmacokinetics of levodopa/carbidopa.

Oral Contraception

Co-administration of rotigotine (3 mg/24 hours) did not affect the pharmacodynamics and pharmacokinetics of oral contraceptives (0.03 mg ethinylestradiol, 0.15 mg levonorgestrel).

Omeprazole

Co-administration of the CYP2C19 selective inhibitor omeprazole (40 mg/day) had no effect on the steady-state pharmacokinetics of rotigotine (4 mg/24 hours).

Pharmacokinetics in Special Populations

Hepatic Impairment

The effect of impaired hepatic function on the pharmacokinetics of rotigotine has been studied in subjects with moderate hepatic impairment (Child-Pugh classification – Grade B). There were no relevant changes in rotigotine plasma concentrations. No information is available on subjects with severe impairment of hepatic function.

Renal Impairment

The effect of renal function on rotigotine pharmacokinetics has been studied in subjects with mild to severe impairment of renal function including subjects requiring dialysis compared to healthy subjects. There were no relevant changes in rotigotine plasma concentrations (up to end-stage renal disease requiring hemodialysis). In subjects with severe renal impairment not on dialysis (i.e., creatinine clearance 15 to less than 30 ml/min), exposure to conjugated rotigotine metabolites was doubled.

Gender

Female and male subjects and patients had similar plasma concentrations (body weight normalized).

Geriatric Patients

Plasma concentrations of rotigotine in patients 65 to 80 years of age were similar to those in younger patients, approximately 40 to 64 years of age. Although not studied, exposures in older subjects (more than 80 years) may be higher due to skin changes with aging.

Pediatric Patients

The pharmacokinetics of rotigotine in subjects below the age of 18 years has not been established.

Race

The pharmacokinetic profile was similar in Caucasians, Blacks, and Japanese.

Adhesion

Adhesion was examined in subjects with Parkinson's disease when patches were applied to rotating sites. Similar results were observed for the 4 mg/24 hours (20 cm^2), 6 mg/24 hours (30 cm^2), and 8 mg/24 hours (40 cm^2) patches. An adherence of 90% or more of the patch surface was observed in 71% to 82% of cases. A partial detachment of more than 10% was observed in 15% to 24% of cases. A complete detachment of the patch was observed in 3% to 5% of cases.

13 NONCLINICAL TOXICOLOGY

13.1 Carcinogenesis, Mutagenesis, Impairment of Fertility

Carcinogenesis

Two-year carcinogenicity studies of rotigotine were conducted in mice at doses of 0, 3, 10, and 30 mg/kg and in rats at doses of 0, 0.3, 1, and 3 mg/kg; in both studies rotigotine was administered subcutaneously once every 48 hours. No significant increases in tumors occurred in mice at doses up to 9 times the maximum recommended human dose (MRHD) in Parkinson's disease (8 mg/24 hours).

In rats, there were increases in Leydig cell tumors and in uterine tumors (adenocarcinomas, squamous cell carcinomas) at all doses. The endocrine mechanisms believed to be involved in the production of these tumors in rats are not considered relevant to humans. Therefore, there were no tumor findings considered relevant to humans at plasma exposures (AUC) up to 4 to 6 times that in humans at the MRHD.

Mutagenesis

Rotigotine was negative in the in vitrobacterial reverse mutation (Ames) and in the in vivomicronucleus assays. Rotigotine was mutagenic and clastogenic in the in vivomouse lymphoma tkassay.

Infertility

When rotigotine was administered subcutaneously (0, 1.5, 5, or 15 mg/kg/day) to female rats prior to and during mating and continuing through gestation day 7, an absence of implantation was observed at all doses. The lowest dose tested is 2 times the MRHD on a mg/m^2basis. In male rats treated from 70 days prior to and during mating, there was no effect on fertility; however, a decrease in epididymal sperm motility was observed at the highest dose tested. The no-effect dose (5 mg/kg/day) is 6 times the MRHD on a mg/m^2basis. When rotigotine was administered subcutaneously to female mice at doses of 0, 10, 30, and 90 mg/kg/day from 2 weeks until 4 days before mating and then at a dose of 6 mg/kg/day (all groups) (approximately 4 times the MRHD on a mg/m^2basis) from 3 days before mating until gestation day 7, a markedly reduced (low dose) or complete absence of implantation (mid and high doses) was observed. The effects on implantation in rodents are thought to be due to the prolactin-lowering effect of rotigotine. In humans, chorionic gonadotropin, not prolactin, is essential for implantation.

13.2 Animal Toxicology and/or Pharmacology

Retinal Pathology: Albino rats

Retinal degeneration was observed in albino rats in a 6-month toxicity study at the highest dose of rotigotine (plasma exposure [AUC] at least 15 times that in humans at the MRHD). Retinal degeneration was not observed in the 2-year carcinogenicity studies in albino rat (plasma AUCs up to 4-6 times that in humans at the MRHD) or albino mouse, or in monkeys treated for 1 year. The potential significance of this effect in humans has not been established, but cannot be disregarded because disruption of a mechanism that is universally present in vertebrates (i.e., disk shedding) may be involved.

14 CLINICAL STUDIES

14.1 Parkinson's Disease

The effectiveness of NEUPRO in the treatment of the signs and symptoms of idiopathic Parkinson's disease was established in five parallel-group, randomized, double-blind, placebo-controlled trials conducted in the U.S. and abroad. Three of these five trials enrolled patients with early-stage Parkinson's disease (not receiving levodopa), and two enrolled patients with advanced-stage Parkinson's disease who were receiving levodopa. Depending on trial design, patients underwent a weekly titration of NEUPRO in 2 mg/24 hours increments to either the randomized dose or optimal dose. Back titrations by 2 mg/24 hours decrement of NEUPRO were permitted for intolerable adverse events. Patch application sites were changed on a daily basis.

Change from baseline in the Unified Parkinson's Disease Rating Scale (UPDRS), Parts II + III, served as the primary outcome assessment measure in the early-stage studies. The UPDRS is a four-part multi-item rating scale intended to evaluate mentation (Part I), Activities of Daily Living (ADL) (Part II), motor performance (Part III), and complications of therapy (Part IV). Part II of the UPDRS contains 13 questions relating to ADL, which are scored from 0 (normal) to 4 (maximal severity) for a maximum (worst) score of 52. Part III of the UPDRS contains 27 questions (for 14 items) and is scored as described for Part II. Part III is designed to assess the severity of the cardinal motor findings in patients with Parkinson's disease (e.g., tremor, rigidity, bradykinesia, postural instability, etc.), scored for different body regions, and has a maximum (worst) score of 108.

Change from baseline in time spent "off" (hours) based on daily diaries was the primary outcome assessment in the two trials of advanced-stage Parkinson's disease (with levodopa).

Studies in Patients with Early-Stage Parkinson's Disease

Patients (N=649) in the three trials of early-stage Parkinson's disease had limited or no prior exposure to levodopa (off levodopa for at least 28 days prior to baseline or levodopa use for no more than 6 months). Patients were excluded from the studies if they had a history of pallidotomy, thalamotomy, deep brain stimulation, or fetal tissue transplant. Patients receiving selegiline, anticholinergic agents, or amantadine must have been on a stable dose and able to maintain that dose for the duration of the study.

PD-1

This trial was a multicenter, multinational, dose-response study in which 316 early-stage Parkinson's disease patients were titrated over 4 weeks to their randomized treatment with either placebo or one of four fixed doses of NEUPRO (2 mg/24 hours, 4 mg/24 hours, 6 mg/24 hours, or 8 mg/24 hours). The patches were applied to the upper abdomen and the sites of application were rotated on a daily basis.

Patients underwent a weekly titration (increasing the number of 2 mg/24 hours patches or placebo patches at weekly intervals) over 4 weeks such that the target doses of NEUPRO were achieved for all groups by the end of 3 weeks and were administered over the fourth week of the titration phase. Patients then continued on treatment for a 7-week maintenance phase followed by a down titration during the last week. Two back titrations by a single patch (i.e., 2 mg/24 hours decrement of NEUPRO or placebo) at a time were permitted for intolerable adverse events. The mean age of patients was approximately 60 years (range 33-83 years; approximately 36% were 65 years or older) and the study enrolled more men (62%) than women (39%). Most patients (85%) were Caucasian and most randomized patients (≥88%) completed the full treatment period.

Mean baseline combined UPDRS (Parts II + III) scores were similar among all treatment groups, between 27.1 and 28.5 for all groups. The mean change from baseline and difference from placebo for each treatment group is shown in Table 5. Statistically significant mean changes reflecting dose-related improvement were observed at the three highest doses, and the 6 mg/24 hours and 8 mg/24 hours doses had a similar effect.

Table 5 PD-1: Mean Change in UPDRS (Parts II + III) from Baseline at End of Treatment for Intent-to-Treat Population
Treatment | Mean Change from Baseline | Difference from Placebo
Placebo | -1.4 | NA
NEUPRO 2 mg/24 hours | -3.5 | -2.1
NEUPRO 4 mg/24 hours | -4.5 | -3.1
NEUPRO 6 mg/24 hours | -6.3 | -4.9
NEUPRO 8 mg/24 hours | -6.3 | -5.0

PD-2

This trial was a multinational, randomized, double-blind, flexible NEUPRO dose (2 mg/24 hours, 4 mg/24 hours, or 6 mg/24 hours), parallel-group study in which 277 early-stage Parkinson's disease patients were assigned (2: 1 ratio) to treatment with NEUPRO or placebo for a period up to about 28 weeks. This trial was conducted in 47 sites in North America (U.S. and Canada). Patches were applied to different body parts including upper or lower abdomen, thigh, hip, flank, shoulder, and/or upper arm and patch application sites were to be rotated on a daily basis. Patients underwent a weekly titration (consisting of 2 mg/24 hours increments at weekly intervals) over 3 weeks to a maximal dose of 6 mg/24 hours depending on efficacy and tolerability, and then received treatment over a 24-week maintenance phase followed by a de-escalation over a period up to 4 days. Back/down titration by a single patch (i.e., 2 mg/24 hours decrement of NEUPRO or placebo) was permitted during the titration phase for intolerable adverse events but was not permitted during the maintenance phase (i.e., patients with intolerable adverse events had to leave the study). Primary efficacy data were collected after a treatment period of up to approximately 27 weeks.

The mean age of patients was approximately 63 years (range 32-86 years; approximately 45% were 65 years or older), approximately two-thirds of all patients were men, and nearly all patients were Caucasian.

Approximately 90% of patients randomized to NEUPRO achieved a maximal daily dose of 6 mg/24 hours; 70% maintained this dose for most (more than 20 weeks) of the maintenance phase. Most enrolled patients (≥81%) completed the full treatment period.

Mean baseline combined UPDRS (Parts II + III) was similar in both groups (29.9 NEUPRO group, 30.0 placebo). NEUPRO-treated patients experienced a mean change in the combined UPDRS (Parts II + III) from baseline to end of treatment (end of treatment week 27 or last visit for patients discontinuing early) of -4.0 (Table 6), and the difference from placebo was statistically significant.

Table 6 PD-2: Mean Change in UPDRS (Parts II + III) from Baseline at End of Treatment for Intent-to-Treat Population
Treatment | Mean Change from Baseline | Difference from Placebo
Placebo | +1.3 | NA
NEUPRO up to 6 mg/24 hours | -4.0 | -5.3

PD-3

This study was a multinational, randomized, double-blind, flexible-dose (NEUPRO 2 mg/24 hours, 4 mg/24 hours, 6 mg/24 hours, or 8 mg/24 hours), three-arm, parallel-group study using a double-dummy treatment in which 561 early-stage Parkinson's disease patients were assigned to treatment with either placebo or NEUPRO or active oral comparator in a ratio of 1: 2: 2 for a period up to about 39 weeks. This study was conducted in up to 81 sites in many countries outside of North America. Patches were applied to different body parts including upper or lower abdomen, thigh, hip, flank, shoulder, and/or upper arm and patch application sites were to be rotated on a daily basis. Treatment with a patch and placebo was given to all patients in a double-blinded manner such that no one would know the actual treatment (i.e., NEUPRO, comparator, or placebo). Patients underwent a weekly dose escalation/titration of patch (consisting of 2 mg/24 hours increments of NEUPRO or placebo) and a dose escalation of capsules of comparator or placebo over 13 weeks (13-week titration was planned for the comparator treatment) up to a maximal dose of 8 mg/24 hours of NEUPRO depending on achieving optimal efficacy or intolerability at a lower dose. Patients randomized to NEUPRO achieved the maximal dose of 8 mg/24 hours after a 4-week titration if maximal efficacy and intolerability had not occurred over a 4-week titration period. Patients then received treatment over a 24-week maintenance phase followed by a de-escalation over a period up to 12 days. A single back titration by a single patch (i.e., 2 mg/24 hours decrement of NEUPRO or placebo) or capsule was permitted during the titration phase for intolerable adverse events but was not permitted during the maintenance phase (i.e., patients with intolerable adverse events had to discontinue from this study). Primary efficacy data were collected after a treatment period of up to approximately 37 weeks of randomized treatment.

The mean age of patients was approximately 61 years (range 30-86 years; approximately 41% were 65 years or older), nearly 60% of all patients were men, and nearly all patients were Caucasian. About 73% of patients completed the full treatment period. The mean daily dose of NEUPRO was just less than 8 mg/24 hours and approximately 90% of patients achieved the maximal daily dose of 8 mg/24 hours.

Mean baseline combined UPDRS (Parts II + III) was similar across all groups (33.2 NEUPRO, 31.3 placebo, 32.2 comparator). NEUPRO-treated patients experienced a mean change in the combined UPDRS (Parts II + III) from baseline to end of treatment (end of treatment week 37 or last visit for patients discontinuing early) of -6.8, and the difference from placebo-treated patients showed a mean change from baseline of -2.3 (see Table 7), a difference that was statistically significant.

Table 7 PD-3: Mean Change in UPDRS (Parts II + III) from Baseline at End of Treatment for Intent-to-Treat Population
Treatment | Mean Change from Baseline | Difference from Placebo
Placebo | -2.3 | NA
NEUPRO up to 8 mg/24 hours | -6.8 | -4.5

Studies in Patients with Advanced-Stage Parkinson's Disease

Patients (N=658) in the three trials of NEUPRO in advanced-stage Parkinson's disease had to be experiencing "on-off" periods at baseline, despite treatment with optimal doses of levodopa. Patients continued concomitant levodopa during the trial; however, reductions in the dosage of levodopa were allowed if patients experienced adverse events that the investigator considered related to dopaminergic therapy. Patients were excluded from the studies if they had a history of pallidotomy, thalamotomy, deep brain stimulation, or fetal tissue transplant.

Patients receiving selegiline, anticholinergic agents, or amantadine must have been on a stable dose and able to maintain that dose for the duration of the study. In the North American trial, COMT-inhibitors were not permitted.

PD-4

This trial was a multinational, three-arm, parallel-group study in which 351 advanced-stage Parkinson's disease patients were titrated over 5 weeks to treatment with either placebo or NEUPRO (8 mg/24 hours or 12 mg/24 hours) and maintained treatment for 24 weeks followed by a down titration over the last week. This study was conducted in 55 sites in North America (U.S. and Canada).

Mean baseline "off" times were similar among all treatment groups (6.4, 6.8, and 6.3 hours for the placebo, NEUPRO 8 mg/24 hours and 12 mg/24 hours treatment groups, respectively). NEUPRO-treated patients experienced a mean change in "off" time from baseline to end of treatment of -2.7 hours for the 8 mg/24 hours treatment arm and -2.1 hours for the 12 mg/24 hours treatment arm (Table 8), and the difference from placebo was statistically significant for both NEUPRO doses (8 mg/24 hours, 12 mg/24 hours). Onset of treatment benefit began as early as the first week of treatment.

Table 8 PD-4: Mean Change in "Off" Time (Hours) from Baseline at End of Treatment for Intent-to-Treat Population
Treatment | Mean Change from Baseline | Difference from Placebo
Placebo | -0.9 | NA
NEUPRO 8 mg/24 hours | -2.7 | -1.8
NEUPRO 12 mg/24 hours | -2.1 | -1.2

PD-5

This trial was a multinational, flexible-dose, three-arm, parallel-group study using a double-dummy treatment in which 506 advanced-stage Parkinson's disease patients were titrated over 7 weeks to treatment with either NEUPRO from a minimum dose of 4 mg/24 hours up to an optimal dose not exceeding 16 mg/24 hours, active oral comparator, or placebo and maintained treatment for 16 weeks followed by a down titration over 6 days.

This study was conducted in 77 sites in many countries outside of North America.

Mean baseline "off" times were similar among all treatment groups (6.6, 6.2, and 6.0 hours for the placebo, NEUPRO, and comparator treatment groups, respectively). NEUPRO-treated patients experienced a mean 2.5 hour decrease change in "off" time from baseline to end of treatment (Table 9), and the difference from placebo was statistically significant. Onset of treatment benefit began as early as the first week of treatment. The optimal NEUPRO dose was established as 4 mg/24 hours for 2% of patients, 6 mg/24 hours for 6%, 8 mg/24 hours for 8%, 10 mg/24 hours for 9%, 12 mg/24 hours for 16%, 14 mg/24 hours for 11% and 16 mg/24 hours for 44%.

Table 9 PD-5: Mean Change in "Off" Time (Hours) from Baseline at End of Treatment for Intent-to-Treat Population
Treatment | Mean Change from Baseline | Difference from Placebo
Placebo | -0.9 | NA
NEUPRO up to 16 mg/24 hours | -2.5 | -1.6

14.2 Restless Legs Syndrome

The clinical program included 1309 patients with moderate-to-severe RLS. The efficacy of NEUPRO in the treatment of Restless Legs Syndrome (RLS) was primarily evaluated in two randomized, double-blind, placebo-controlled, fixed-dose trials with maintenance periods of 6 months duration. Patients received NEUPRO doses ranging from 0.5 mg/24 hours to 3 mg/24 hours or placebo once daily. In these two trials, the mean duration of RLS was 2.1 to 3.1 years, mean age was approximately 55 years (range 19-78 years), approximately 68% were women, and 97% were Caucasian. In both trials, patches were applied to different application sites including the abdomen, thigh, hip, flank, shoulder, and/or upper arm and patch application sites were rotated on a daily basis.

The two outcome measures used to assess the effect of treatment as co-primary efficacy endpoints were the International RLS Rating Scale (IRLS Scale) and a Clinical Global Impression - Improvement (CGI-I) assessment. The IRLS Scale contains 10 items designed to assess the severity of sensory and motor symptoms, sleep disturbance, daytime somnolence, and impact on activities of daily living and mood associated with RLS. The range of scores is 0 to 40, with 0 being absence of RLS symptoms and 40 the most severe symptoms. The CGI-I is designed to assess clinical progress (global improvement) on a 7-point scale.

RLS-1

This trial was a multicenter, five-arm, parallel-group, fixed-dose trial of NEUPRO in subjects with moderate-to-severe RLS. A total of 505 subjects were randomized in this trial, participating at approximately 50 sites in the U.S. Subjects received placebo or NEUPRO (0.5 mg/24 hours, 1 mg/24 hours, 2 mg/24 hours, 3 mg/24 hours). Subjects began treatment at a daily dosage of 0.5 mg/24 hours NEUPRO and were titrated over a 4-week period to their assigned daily dose followed by a 6-month maintenance period and 7-day down titration period.

Mean baseline IRLS sum score were similar among all treatment groups (23.5, 23.1, 23.2, 23.3, and 23.6 for the placebo, NEUPRO 0.5 mg/24 hours, 1 mg/24 hours, 2 mg/24 hours, and 3 mg/24 hours groups, respectively).

Patients experienced a mean change in the IRLS sum score from baseline to the end of treatment for each of the four NEUPRO dose groups. The mean changes from baseline and differences from placebo in IRLS sum score and CGI Item 1 are shown for each treatment group in Table 10. The difference between the two highest treatment groups (2 mg/24 hours and 3 mg/24 hours) and placebo were statistically significant. Of the NEUPRO-treated patients, 23% had an IRLS score of 0 compared to 9.1% of placebo patients at the end of the maintenance period. Onset of treatment benefit was seen with the 1 mg/24 hours dose.

Table 10 RLS-1: ANCOVA Results for Co-primary Endpoints: Change from Baseline to End of Maintenance Period for Intent-to-Treat Population
Variable | Treatment | Mean Change from Baseline | Difference from Placebo
IRLS sum score | Placebo | -9.0 | NA
IRLS sum score | NEUPRO 0.5 mg/24 hours | -11.1 | -2.2
IRLS sum score | NEUPRO 1 mg/24 hours | -11.2 | -2.3
IRLS sum score | NEUPRO 2 mg/24 hours | -13.5 | -4.5
IRLS sum score | NEUPRO 3 mg/24 hours | -14.2 | -5.2
CGI Item 1 | Placebo | -1.4 | NA
CGI Item 1 | NEUPRO 0.5 mg/24 hours | -1.8 | -0.35
CGI Item 1 | NEUPRO 1 mg/24 hours | -1.7 | -0.32
CGI Item 1 | NEUPRO 2 mg/24 hours | -2.1 | -0.65
CGI Item 1 | NEUPRO 3 mg/24 hours | -2.3 | -0.90

RLS-2

This trial was a multicenter, four-arm, parallel-group trial of NEUPRO in subjects with moderate-to-severe RLS. A total of 458 subjects were randomized in this trial, participating at approximately 50 sites in 8 European countries. Patients received placebo or NEUPRO (1 mg/24 hours, 2 mg/24 hours, 3 mg/24 hours). Patients began treatment at a daily dosage of 1 mg/24 hours NEUPRO and were titrated over a 3-week period to their assigned daily dose followed by a 6-month maintenance period and 7-day down-titration period.

Mean baseline IRLS sum score were similar among all treatment groups (28.1, 28.1, 28.2, and 28.0 for the placebo, NEUPRO 1 mg/24 hours, 2 mg/24 hours, and 3 mg/24 hours groups, respectively). Patients experienced a mean change in the IRLS sum score from baseline to the end of treatment for each of the three NEUPRO dose groups. The mean changes from baseline and differences from placebo in IRLS sum score and CGI Item 1 are shown for each treatment group in Table 11. The difference between all three treatment groups (1 mg/24 hours, 2 mg/24 hours, and 3 mg/24 hours) and placebo were statistically significant. Of the NEUPRO-treated patients, 24% had an IRLS score of 0 compared to 12% of placebo patients at the end of the maintenance period. Onset of treatment benefit was seen with the 1 mg/24 hours dose.

Table 11 RLS-2: ANCOVA Results for Co-primary Endpoints: Change from Baseline to End of Maintenance Period for Intent-to-Treat Population
Variable | Treatment | Mean Change from Baseline | Difference from Placebo
IRLS sum score | Placebo | -8.6 | NA
IRLS sum score | NEUPRO 1 mg/24 hours | -13.7 | -5.1
IRLS sum score | NEUPRO 2 mg/24 hours | -16.2 | -7.5
IRLS sum score | NEUPRO 3 mg/24 hours | -16.8 | -8.2
CGI Item 1 | Placebo | -1.3 | NA
CGI Item 1 | NEUPRO 1 mg/24 hours | -2.0 | -0.76
CGI Item 1 | NEUPRO 2 mg/24 hours | -2.4 | -1.07
CGI Item 1 | NEUPRO 3 mg/24 hours | -2.5 | -1.21

16 HOW SUPPLIED/STORAGE AND HANDLING

Each transdermal system is packaged in a separate pouch.

Each strength is available in cartons of 30 transdermal systems.

1 mg/24 hours | 30 transdermal systems | NDC #50474-801-03
2 mg/24 hours | 30 transdermal systems | NDC #50474-802-03
3 mg/24 hours | 30 transdermal systems | NDC #50474-803-03
4 mg/24 hours | 30 transdermal systems | NDC #50474-804-03
6 mg/24 hours | 30 transdermal systems | NDC #50474-805-03
8 mg/24 hours | 30 transdermal systems | NDC #50474-806-03

STORAGE AND HANDLING

Store at 20º - 25ºC (68º - 77ºF); excursions permitted between 15º - 30ºC (59º - 86ºF). [See USP Controlled Room Temperature]

NEUPRO should be stored in the original pouch. Do not store outside of pouch.

Apply the transdermal system immediately upon removal from the pouch. Discard used systems in household trash in a manner that prevents accidental application or ingestion by children, pets, or others.

17 PATIENT COUNSELING INFORMATION

Advise the patient to read the FDA-approved patient labeling (Patient Information).

Sulfite Sensitivity

Advise patients about potential for sulfite sensitivity. NEUPRO contains sodium metabisulfite, which may cause allergic-type reactions including anaphylactic symptoms and life-threatening or less severe asthmatic episodes in certain susceptible people. An allergy to sulfites is not the same as an allergy to sulfa [see Warnings and Precautions (5.1)] .

Falling Asleep During Activities of Daily Living and Somnolence

Advise and alert patients about the potential for sedating effects associated with NEUPRO, including somnolence and particularly to the possibility of falling asleep while engaged in activities of daily living. Because somnolence can be a frequent adverse reaction with potentially serious consequences, patients should neither drive a car nor engage in other potentially dangerous activities until they have gained sufficient experience with NEUPRO to gauge whether or not it affects their mental and/or motor performance adversely. Advise patients that if increased somnolence or new episodes of falling asleep during activities of daily living (e.g., watching television, passenger in a car, etc.) are experienced at any time during treatment, they should not drive or participate in potentially dangerous activities until they have contacted their physician. Patients should not drive, operate machinery, or work at heights during treatment if they have previously experienced somnolence and/or have fallen asleep without warning prior to use of NEUPRO.

Because of the possible additive effects, caution should also be used when patients are taking alcohol, sedating medications, or other CNS depressants (e.g., benzodiazepines, antipsychotics, antidepressants, etc.) in combination with NEUPRO [see Warnings and Precautions (5.2)] .

Hallucinations/Psychosis

Inform patients that hallucinations and other symptoms of psychosis can occur while taking NEUPRO. In patients with Parkinson's disease, the elderly are at a higher risk than younger patients [see Warnings and Precautions (5.3)] .

Symptomatic Hypotension

Advise patients that they may develop symptomatic (or asymptomatic) hypotension while taking NEUPRO. Hypotension may occur more frequently during initial therapy. Accordingly, caution patients against rising rapidly after sitting or lying down, especially if they have been doing so for prolonged periods and especially at the initiation of treatment with NEUPRO [see Warnings and Precautions (5.4)] .

Syncope

Advise patients about the potential for syncope in patients using dopamine agonists. For this reason, alert patients to the possibility of syncope while taking NEUPRO [see Warnings and Precautions (5.5)] .

Impulse Control/Compulsive Behaviors

Advise patients that they may experience impulse control and/or compulsive behaviors and dopamine dysregulation syndrome while taking NEUPRO. Ask patients and advise them to inform their physicians about the development of new or increased gambling urges, sexual urges, other urges, or repeated use of more NEUPRO than as prescribed to manage their symptoms [see Warnings and Precautions (5.6)] .

Elevation of Blood Pressure and Heart Rate

Advise patients that NEUPRO can increase blood pressure and heart rate [see Warnings and Precautions (5.7)] .

Weight Gain and Fluid Retention

Advise patients that NEUPRO can cause increased weight and fluid retention [see Warnings and Precautions (5.8)] .

Dyskinesia

Inform patients that NEUPRO may cause or exacerbate pre-existing dyskinesia [see Warnings and Precautions (5.9)] .

Application Site Reactions

Inform patients that application site reactions can occur and that the NEUPRO transdermal system application site should be rotated on a daily basis. NEUPRO should not be applied to the same application site more than once every 14 days. Advise patients to report persistent application site reaction (of more than a few days), increases in severity, or skin reactions that spread outside the application site to their physician [see Warnings and Precautions (5.10)] .

If there is a skin rash or irritation from the transdermal system, direct sunlight on the area should be avoided until the skin heals. Exposure could lead to changes in the skin color.

Augmentation and Rebound in RLS

Inform patients that NEUPRO may cause RLS symptoms to have an earlier onset during the day or become worse [see Warnings and Precautions (5.11)] .

Magnetic Resonance Imaging and Cardioversion

Inform patients to remove NEUPRO before undergoing magnetic resonance imaging (MRI) or cardioversion. These procedures could cause a burn to the site where NEUPRO is applied [see Warnings and Precautions (5.12)] .

Heat Application

Advise patients about the potential for heat application to increase drug absorption. Because applying external heat (e.g., a heating pad, sauna, or hot bath) to the transdermal system may increase the amount of drug absorbed, instruct patients to avoid applying heating pads or other sources of heat to the area of the transdermal system. Direct sun exposure of the transdermal system should also be avoided [see Warnings and Precautions (5.13)] .

Nausea, Vomiting, and Dyspepsia

Inform patients that NEUPRO causes nausea, vomiting, and general gastrointestinal distress (i.e., dyspepsia/abdominal discomfort). Nausea and vomiting may occur more frequently during initial therapy and may require dose adjustment.

Withdrawal-Emergent Hyperpyrexia and Confusion

Advise patients who have been prescribed a lower dose or who have been withdrawn from the drug to notify their healthcare provider if they have symptoms such as fever, muscular rigidity, or altered consciousness [see Warnings and Precautions (5.14)] .

Withdrawal Symptoms

Advise patients that withdrawal symptoms may occur during or after discontinuation or dose reduction of NEUPRO. Advise patients who have been prescribed a lower dose or who have been withdrawn from the drug to notify their healthcare provider if they have withdrawal symptoms such as apathy, anxiety, depression, fatigue, insomnia, sweating, or pain. Notify patients that in case of severe withdrawal symptoms, a trial re-administration of a dopamine agonist at the lowest effective dose may be considered [see Warnings and Precautions (5.15)] .

Pregnancy

Because the teratogenic potential of rotigotine has not been completely established in laboratory animals, and because experience in humans is limited, advise women to notify their physicians if they become pregnant or intend to become pregnant during therapy [see Use in Specific Populations (8.1)].

Lactation

Because of the possibility that rotigotine may be excreted in breast milk, advise women to notify their physicians if they intend to breastfeed or are breastfeeding an infant [see Use in Specific Populations (8.2)].

Instructions for Use

Instruct patients to wear NEUPRO continuously for 24 hours. After 24 hours, the patch should be removed and a new one applied immediately. Patients can choose the most convenient time of day or night to apply NEUPRO but should be advised to apply the patch at approximately the same time each day. If a patient forgets to change a patch, a new patch should be applied as soon as possible and replaced at the usual time the following day. Advise patients that they should only discontinue use of NEUPRO under the supervision of a healthcare professional to reduce the risk for hyperpyrexia and confusion associated with sudden discontinuation or dose reduction.

The application site for NEUPRO should be moved on a daily basis (for example, from the right side to the left side and from the upper body to the lower body). NEUPRO should not be applied to the same application site more than once every 14 days.

NEUPRO should be applied immediately after opening the pouch and removing the protective liner. The system should be pressed firmly in place for 30 seconds, making sure there is good contact, especially around the edges.

NEUPRO should be applied once daily to clean, dry, and intact skin on the abdomen, thigh, hip, flank, shoulder, or upper arm. Shave hairy areas at least 3 days prior to applying the patch. Do not apply to areas that could be rubbed by tight clothing, or under a waistband, to skin folds, or to skin that is red or irritated. Creams, lotions, ointments, oils, and powders should not be applied to the skin area where NEUPRO will be placed. Patients should wash their hands to remove any drug and should be careful not to touch their eyes or any objects [see Dosage and Administration (2)] .

Instruct patients not to cut or damage NEUPRO.

Care should be used to avoid dislodging the patch while showering, bathing or during physical activity. If the edges of the patch lift, NEUPRO may be taped down with bandage tape. If the patch detaches, a new one may be applied immediately to a different site. The patient should then change the patch according to their regular schedule.

Removal of the patch

NEUPRO should always be removed slowly and carefully to avoid irritation. After removal, the patch should be folded over so that it sticks to itself and should be discarded so that children and pets cannot reach it. Wash the site with soap and water to remove any drug or adhesive. Baby or mineral oil may be used to remove any excess residue. Alcohol and other solvents (such as nail polish remover) may cause skin irritation and should not be used.

Manufactured for:
UCB, Inc.
Smyrna, GA 30080

Neupro®is a registered trademark of the UCB Group of Companies.
©2021 UCB, Inc., Smyrna, GA 30080. All rights reserved.

PATIENT INFORMATION NEUPRO®[NU pro] (rotigotine transdermal system)

If you have Parkinson's disease, read this side. If you have Restless Legs Syndrome (also known as Willis-Ekbom disease), read the other side.

Rx Only

IMPORTANT: NEUPRO is for use on the skin only.

What is NEUPRO?

NEUPRO is a prescription medicine used to treat Parkinson's disease (PD). NEUPRO is a patch worn on the skin.

It is not known if NEUPRO is safe and effective in children.

Who should not use NEUPRO?

Do notuse NEUPRO if you are allergic to rotigotine or any of the ingredients in NEUPRO. See the end of this leaflet for a complete list of ingredients in NEUPRO.

What should I tell my doctor before using NEUPRO?

Before you start using NEUPRO, tell your doctor if you:

- have breathing problems including asthma.
- have daytime sleepiness from a sleep disorder or have unexpected or unpredictable sleepiness or periods of sleep.
- have mental problems such as schizophrenia, bipolar disorder, or psychosis.
- feel dizzy, nauseated, sweaty, or faint when you stand up from sitting or lying down.
- drink alcoholic beverages. This may increase your chances of becoming drowsy or sleepy while using NEUPRO.
- have high or low blood pressure.
- have or have had heart problems.
- are pregnant or plan to become pregnant. It is not known if NEUPRO will harm your unborn baby.
- are breastfeeding or plan to breastfeed. It is not known if NEUPRO passes into your breastmilk. The amount of breast milk you make may be decreased while taking NEUPRO. Talk to your doctor about the best way to feed your baby if you take NEUPRO.

Tell your doctor about all the medicines you take,including prescription and over-the-counter medicines, vitamins, and herbal supplements.

NEUPRO and other medicines may affect each other causing side effects. NEUPRO may affect the way other medicines work, and other medicines may affect how NEUPRO works.

Especially tell your doctor if you take other medicines that can make you sleepy such as sleep medicines, antidepressants, or antipsychotics.

Know the medicines you take. Keep a list of them to show your doctor and pharmacist when you get a new medicine.

How should I use NEUPRO for Parkinson's disease?

- Read the Instructions for Use at the end of this leaflet for specific information about the right way to apply the NEUPRO patch.
- Use NEUPRO exactly as your doctor tells you to use it.
- NEUPRO comes in 4 different size (dose) patches for Parkinson's disease. Your doctor should start you on a low dose of NEUPRO. Your doctor will change the dose weekly until you are taking the right amount of medicine to control your symptoms. It may take several weeks before you reach the dose that controls your symptoms best.
- Apply NEUPRO 1 time each day at the same time each day.
- You may bathe, shower, or swim while wearing a NEUPRO patch. Water may loosen your NEUPRO patch.
- If the edges of the patch lift, you may tape them down with bandaging tape.
- If your NEUPRO patch falls off, apply a new NEUPRO patch for the rest of the day. The next day, apply a new patch at your regular time.
- If you miss a dose or forget to change your NEUPRO patch, apply a new NEUPRO patch as soon as you remember. Replace the NEUPRO patch at your normal time the next day.
- Do notstop using NEUPRO without talking to your doctor first. If your doctor tells you to stop using NEUPRO, you should ask your doctor for specific instructions on how to slowly and safely discontinue using NEUPRO. If you stop using NEUPRO, you may have withdrawal symptoms (see " What are the possible side effects of NEUPRO?").

What should I avoid while using NEUPRO?

- Do notdrive, operate machinery, or do other dangerous activities until you know how NEUPRO affects you.
- Avoid exposing the site where you have applied your NEUPRO patch to heating pads, electric blankets, heat lamps, saunas, hot tubs, heated water beds, and direct sunlight. Too much medicine could be absorbed into your body.
- Do notuse NEUPRO during certain medical procedures called magnetic resonance imaging (MRI) or cardioversion. Using NEUPRO during these procedures could cause a burn to the site where you applied your NEUPRO patch.
- Avoid direct sunlight if you get a skin rash or irritation from NEUPRO until your skin heals. Sun exposure could lead to skin color changes.

What are the possible side effects of NEUPRO?

NEUPRO can cause serious side effects, including:

- severe allergic reactions.NEUPRO contains a sulfite called sodium metabisulfite. Sulfites can cause severe allergic reactions that are life threatening to some people who are sensitive to sulfites. An allergy to sulfites is not the same as an allergy to sulfa. People with asthma are more likely to be allergic to sulfites. Remove your NEUPRO patch right away and call your doctor if you have swelling of the lips or tongue, chest pain, trouble breathing or swallowing.
- falling asleep during normal activities.You may fall asleep while doing normal activities such as driving a car, doing physical tasks, or using hazardous machinery while taking NEUPRO. You may suddenly fall asleep without being drowsy or without warning. This may result in having accidents. Your chances of falling asleep while doing normal activities while using NEUPRO are greater if you take other medicines that cause drowsiness. Tell your doctor right away if this happens. Before starting NEUPRO, be sure to tell your doctor if you take any medicines that make you drowsy.
- hallucinations and other psychosis.NEUPRO can cause or worsen psychotic symptoms including hallucinations (seeing or hearing things that are not real), confusion, excessive suspicion, aggressive behavior, agitation, delusional beliefs (believing things that are not real), and disorganized thinking. The chances of having hallucinations or these other psychotic-like changes are higher in people with Parkinson's disease who are elderly, taking NEUPRO, or taking higher doses of NEUPRO. If you have hallucinations or any of these other psychotic-like changes, talk with your doctor.
- changes in blood pressure.NEUPRO can decrease or increase your blood pressure. Lowering of your blood pressure is of special concern. If you faint or feel dizzy, nauseated, or sweaty when you stand up from sitting or lying down, this may mean that your blood pressure is decreased. If you notice this, you should contact your doctor. Also, when changing position from lying down or sitting to standing up, you should do it carefully and slowly. Lowering of your blood pressure can happen, especially when you start taking NEUPRO or when your dose is increased.
- fainting.Fainting can occur, and sometimes your heart rate may be decreased. This can happen especially when you start using NEUPRO or your dose is increased. Tell your doctor if you faint or feel dizzy.
- unusual urges.Some patients using NEUPRO get urges to behave in a way unusual for them. Examples of this are an unusual urge to gamble, strong urges to spend money, binge eating, or increased sexual urges and behaviors. Some patients may want to use more NEUPRO than prescribed for their symptoms (dopamine dysregulation syndrome). If you notice or your family notices that you are developing any unusual behaviors, talk to your doctor.
- changes in heart rate. NEUPRO can increase your heart rate.
- increased weight and fluid retentioncan occur in patients using NEUPRO. NEUPRO can cause your body to keep extra fluid which leads to swelling and weight gain. Tell your doctor if you have swelling or fluid retention, especially in the ankles or legs, or have an unusually fast increase in weight.
- uncontrolled, sudden movements.NEUPRO may cause uncontrolled, sudden movements or make such movements you already have worse or more frequent. Tell your doctor if this happens. The doses of your anti-Parkinson's medicine may need to be changed.
- skin site reactions.Skin reactions may occur at the site where you apply NEUPRO. Tell your doctor if you get a rash, redness, swelling, or itching that will not go away at the skin site where you have applied NEUPRO.
- withdrawal symptoms.NEUPRO is a dopamine agonist medicine. Dopamine agonist medicines, including NEUPRO, can cause withdrawal symptoms as your dose is slowly lowered (tapered) or when treatment with NEUPRO is stopped. Tell your doctor right away if you get any of the following withdrawal symptoms:
  - fever
  - confusion
  - severe muscle stiffness
  - feeling like you do not care things you usually care about (apathy)
  - anxiety
  - depression
  - fatigue
  - insomnia
  - sweating
  - pain

The most common side effects of NEUPRO for Parkinson's disease are nausea, vomiting, sleepiness, application site reactions, dizziness, loss of appetite, difficulty falling asleep and staying asleep, increased sweating, vision problems, leg swelling, and uncontrolled, sudden movements of arms or legs.

Tell your doctor if you have any side effect that bothers you or that does not go away.

These are not all the possible side effects of NEUPRO. For more information, ask your doctor or pharmacist.

Call your doctor for medical advice about side effects. You may report side effects to FDA at 1-800-FDA-1088.

How should I store NEUPRO?

- Store NEUPRO at 68°F to 77°F (20°C to 25°C).
- Store NEUPRO in its original sealed pouch until use. Do notstore NEUPRO outside of the pouch.

Keep NEUPRO and all medicines out of reach of children and away from pets.

General information about the safe and effective use of NEUPRO.

Medicines are sometimes prescribed for purposes other than those listed in a Patient Information leaflet. Do not use NEUPRO for a condition for which it was not prescribed. Do not give NEUPRO to other people even if they have the same symptoms you have. It may harm them.

This Patient Information leaflet summarizes the most important information about NEUPRO. If you would like more information, talk with your doctor. You can ask your pharmacist or doctor for information about NEUPRO that was written for health professionals.

For more information, go to www.neupro.com or call 1-844-599-2273.

What are the ingredients in NEUPRO?

Active ingredient:rotigotine

Inactive ingredients:ascorbyl palmitate, povidone, silicone adhesive, sodium metabisulfite, and dl-alpha-tocopherol.

INSTRUCTIONS FOR USE
NEUPRO®[NU pro]
(rotigotine transdermal system)

When to apply NEUPRO:

Each NEUPRO patch is sealed in a pouch that protects it until you are ready to apply it. See Figure A.

- NEUPRO should be applied right away after removing it from the protective pouch. Do notdamage or cut your NEUPRO patch into smaller pieces.
- Choose the time of day or night that works best for you to apply your NEUPRO patch. Apply your NEUPRO patch at the same time each day.
- Wear your NEUPRO patch for 24 hours.
- After 24 hours, remove your NEUPRO patch and apply a new one right away to a different area of your skin.

Where to apply NEUPRO:

- Choose an area of clean, dry, and healthy skin on the stomach, thigh, hip, side of the body between the ribs and the pelvis (flank), shoulder, or upper arm. See Figure B.
- Apply your NEUPRO patch to a different place on your skin each day, for example, from the right side to the left side and from the upper body to the lower body. Your NEUPRO patch should not be applied to the same area of your skin more than 1 time every 14 days. Apply NEUPRO to a different area of skin (only one of the shaded areas in Figure B)each day to reduce the chance of getting skin irritation.
- If you need to apply your NEUPRO patch to a hairy area, the area should be shaved at least 3 days before applying the patch.
- Avoid applying your NEUPRO patch to areas where it could be rubbed by tight clothing or under a waistband.
- Avoid applying your NEUPRO patch on skin folds.
- Do notapply your NEUPRO patch to skin that is red, irritated, or injured.
- Avoid applying creams, lotions, ointments, oils, and powders to the skin area where your NEUPRO patch will be placed.

How to apply NEUPRO:

Step 1. | Grasp the two sides of the pouch and pull apart. See Figures Cand D.

Step 2. | Remove your NEUPRO patch from the pouch. See Figure E.

Step 3. | Hold your NEUPRO patch with both hands, with the protective liner on top. See Figure F.

Step 4. | Bend the edges of your NEUPRO patch away from you so that the S-shaped cut in the liner opens up. See Figure G.

Step 5. | Peel off one half of the protective liner. Do nottouch the sticky surface of your NEUPRO patch because the medicine could come off on your fingers. See Figure H.

Step 6. | Apply the sticky half of your NEUPRO patch to a clean area of your skin and remove the remaining liner. See Figures Iand J.

Step 7. | Press your NEUPRO patch firmly with the palm of your hand for 30seconds to make sure there is good contact with your skin, especially around the edges. The warmth of your hand helps the adhesive on the patch to stick to your skin. Make sure that your NEUPRO patch is flat against your skin. There should be no bumps or folds in your NEUPRO patch. See Figure K.

Step 8. | Wash your hands with soap and water right after handling your NEUPRO patch to remove any medicine that may have gotten on them. Do nottouch your eyes until after you have washed your hands.

How to remove NEUPRO:

- Slowly and carefully peel off your used NEUPRO patch. Carefully fold it in half (sticky sides together) and throw away the folded patch so that children and pets cannot reach it. Your NEUPRO patch still contains some medicine and could harm a child or pet.
- Gently wash the area with warm water and mild soap to remove any sticky material (adhesive) that stays on your skin.
- Baby or mineral oil may also be used to remove any adhesive. Avoid using alcohol or other solvents, such as nail polish remover. They may cause your skin to become irritated.
- Wash your hands with soap and water.
- You may see mild redness at the site when a patch is removed like when you remove an adhesive bandage. This redness should go away over time. If irritation or itchiness continues, tell your doctor.

This Patient Package Insert and Instructions for Use has been approved by the U.S. Food and Drug Administration.

Manufactured for: UCB, Inc., Smyrna, GA 30080

Neupro®is a registered trademark of the UCB Group of Companies.
©2021 UCB, Inc., Smyrna, GA 30080. All rights reserved.

Rev. 7/2021

PATIENT INFORMATION
NEUPRO®[NU pro]
(rotigotine transdermal system)

If you have Restless Legs Syndrome (also known as Willis-Ekbom disease), read this side. If you have Parkinson's disease, read the other side.

Rx Only

IMPORTANT: NEUPRO is for use on the skin only.

What is NEUPRO?

NEUPRO is a prescription medicine used to treat moderate-to-severe primary Restless Legs Syndrome (RLS). NEUPRO is a patch worn on the skin.

It is not known if NEUPRO is safe and effective in children.

Who should not use NEUPRO?

Do notuse NEUPRO if you are allergic to rotigotine or any of the ingredients in NEUPRO. See the end of this leaflet for a complete list of ingredients in NEUPRO.

What should I tell my doctor before using NEUPRO?

Before you start using NEUPRO, tell your doctor if you:

- have breathing problems including asthma.
- have daytime sleepiness from a sleep disorder or have unexpected or unpredictable sleepiness or periods of sleep.
- have mental problems such as schizophrenia, bipolar disorder, or psychosis.
- feel dizzy, nauseated, sweaty, or faint when you stand up from sitting or lying down.
- drink alcoholic beverages. This may increase your chances of becoming drowsy or sleepy while using NEUPRO.
- have high or low blood pressure.
- have or have had heart problems.
- are pregnant or plan to become pregnant. It is not known if NEUPRO will harm your unborn baby.
- are breastfeeding or plan to breastfeed. It is not known if NEUPRO passes into your breastmilk. The amount of breast milk you make may be decreased while taking NEUPRO. Talk to your doctor about the best way to feed your baby if you take NEUPRO.

Tell your doctor about all the medicines you take,including prescription and over-the-counter medicines, vitamins, and herbal supplements.

NEUPRO and other medicines may affect each other causing side effects. NEUPRO may affect the way other medicines work, and other medicines may affect how NEUPRO works.

Especially tell your doctor if you take other medicines that can make you sleepy such as sleep medicines, antidepressants, or antipsychotics.

Know the medicines you take. Keep a list of them to show your doctor and pharmacist when you get a new medicine.

How should I use NEUPRO for RLS?

- Read the Instructions for Use at the end of this leaflet for specific information about the right way to apply the NEUPRO patch.
- Use NEUPRO exactly as your doctor tells you to use it.
- NEUPRO comes in 3 different size (dose) patches for RLS. Your doctor should start you on the lowest dose of NEUPRO. Your doctor may change the dose weekly until you are taking the right amount of medicine to control your symptoms. It may take several weeks before you reach the dose that controls your symptoms best.
- Apply NEUPRO 1 time each day at the same time each day.
- You may bathe, shower, or swim while wearing a NEUPRO patch. Water may loosen your NEUPRO patch.
- If the edges of the patch lift, you may tape them down with bandaging tape.
- If your NEUPRO patch falls off, apply a new NEUPRO patch for the rest of the day. The next day, apply a new patch at your regular time.
- If you miss a dose or forget to change your NEUPRO patch, apply a new NEUPRO patch as soon as you remember. Replace the NEUPRO patch at your normal time the next day.
- Do notstop using NEUPRO without talking to your doctor first. If your doctor tells you to stop using NEUPRO, you should ask your doctor for specific instructions on how to slowly and safely discontinue using NEUPRO. If you stop using NEUPRO, you may have withdrawal symptoms (see " What are the possible side effects of NEUPRO?").

What should I avoid while using NEUPRO?

- Do notdrive, operate machinery, or do other dangerous activities until you know how NEUPRO affects you.
- Avoid exposing the site where you have applied your NEUPRO patch to heating pads, electric blankets, heat lamps, saunas, hot tubs, heated water beds, and direct sunlight. Too much medicine could be absorbed into your body.
- Do notuse NEUPRO during certain medical procedures called magnetic resonance imaging (MRI) or cardioversion. Using NEUPRO during these procedures could cause a burn to the site where you applied your NEUPRO patch.
- Avoid direct sunlight if you get a skin rash or irritation from NEUPRO until your skin heals. Sun exposure could lead to skin color changes.

What are the possible side effects of NEUPRO?

NEUPRO can cause serious side effects, including:

- severe allergic reactions.NEUPRO contains a sulfite called sodium metabisulfite. Sulfites can cause severe allergic reactions that are life threatening to some people who are sensitive to sulfites. An allergy to sulfites is not the same as an allergy to sulfa. People with asthma are more likely to be allergic to sulfites. Remove your NEUPRO patch right away and call your doctor if you have swelling of the lips or tongue, chest pain, trouble breathing or swallowing.
- falling asleep during normal activities.You may fall asleep while doing normal activities such as driving a car, doing physical tasks, or using hazardous machinery while taking NEUPRO. You may suddenly fall asleep without being drowsy or without warning. This may result in having accidents. Your chances of falling asleep while doing normal activities while using NEUPRO are greater if you take other medicines that cause drowsiness. Tell your doctor right away if this happens. Before starting NEUPRO, be sure to tell your doctor if you take any medicines that make you drowsy.
- hallucinations and other psychosis. NEUPRO can cause psychotic symptoms including hallucinations (seeing or hearing things that are not real), confusion, excessive suspicion, aggressive behavior, agitation, delusional beliefs (believing things that are not real), and disorganized thinking. If you have hallucinations or any of these other psychotic-like changes, talk with your doctor right away.
- changes in blood pressure.NEUPRO can decrease or increase your blood pressure. Lowering of your blood pressure is of special concern. If you faint or feel dizzy, nauseated, or sweaty when you stand up from sitting or lying down, this may mean that your blood pressure is decreased. If you notice this, you should contact your doctor. Also, when changing position from lying down or sitting to standing up, you should do it carefully and slowly. Lowering of your blood pressure can happen, especially when you start taking NEUPRO or when your dose is increased.
- fainting.Fainting can occur, and sometimes your heart rate may be decreased. This can happen especially when you start using NEUPRO or your dose is increased. Tell your doctor if you faint or feel dizzy.
- unusual urges.Some patients using NEUPRO get urges to behave in a way unusual for them. Examples of this are an unusual urge to gamble, strong urges to spend money, binge eating, or increased sexual urges and behaviors. Some patients may want to use more NEUPRO than prescribed for their symptoms (dopamine dysregulation syndrome). If you notice or your family notices that you are developing any unusual behaviors, talk to your doctor.
- changes in heart rate.NEUPRO can increase your heart rate.
- skin site reactions.Skin reactions may occur at the site where you apply NEUPRO. Tell your doctor if you get a rash, redness, swelling, or itching that will not go away at the skin site where you have applied NEUPRO.
- changes in Restless Legs Syndrome symptoms. NEUPRO may cause Restless Legs Syndrome symptoms to come back (rebound), or become worse or start earlier in the day. The most common side effects of NEUPRO for Restless Legs Syndrome (RLS) are application site reactions, nausea, difficulty falling asleep and staying asleep, sleepiness, and headache.
- withdrawal symptoms.NEUPRO is a dopamine agonist medicine. Dopamine agonist medicines, including NEUPRO, can cause withdrawal symptoms as your dose is slowly lowered (tapered) or when treatment with NEUPRO is stopped. Tell your doctor right away if you get any of the following withdrawal symptoms:
  - fever
  - confusion
  - severe muscle stiffness
  - feeling like you do not care things you usually care about (apathy)
  - anxiety
  - depression
  - fatigue
  - insomnia
  - sweating
  - pain

Tell your doctor if you have any side effect that bothers you or that does not go away.

These are not all the possible side effects of NEUPRO. For more information, ask your doctor or pharmacist.

Call your doctor for medical advice about side effects. You may report side effects to FDA at 1-800-FDA-1088.

How should I store NEUPRO?

- Store NEUPRO at 68°F to 77°F (20°C to 25°C).
- Store NEUPRO in its original sealed pouch until use. Do notstore NEUPRO outside of the pouch.

Keep NEUPRO and all medicines out of reach of children and away from pets.

General information about the safe and effective use of NEUPRO.

Medicines are sometimes prescribed for purposes other than those listed in a Patient Information leaflet. Do not use NEUPRO for a condition for which it was not prescribed. Do not give NEUPRO to other people even if they have the same symptoms you have. It may harm them.

This Patient Information leaflet summarizes the most important information about NEUPRO. If you would like more information, talk with your doctor. You can ask your pharmacist or doctor for information about NEUPRO that was written for health professionals.

For more information, go to www.neupro.com or call 1-844-599-2273.

What are the ingredients in NEUPRO?

Active ingredient:rotigotine

Inactive ingredients:ascorbyl palmitate, povidone, silicone adhesive, sodium metabisulfite, and dl-alpha-tocopherol.

INSTRUCTIONS FOR USE
NEUPRO®[NU pro]
(rotigotine transdermal system)

When to apply NEUPRO:

Each NEUPRO patch is sealed in a pouch that protects it until you are ready to apply it. See Figure A.

- NEUPRO should be applied right away after removing it from the protective pouch. Do notdamage or cut your NEUPRO patch into smaller pieces.
- Choose the time of day or night that works best for you to apply your NEUPRO patch. Apply your NEUPRO patch at the same time each day.
- Wear your NEUPRO patch for 24 hours.
- After 24 hours, remove your NEUPRO patch and apply a new one right away to a different area of your skin.

Where to apply NEUPRO:

- Choose an area of clean, dry, and healthy skin on the stomach, thigh, hip, side of the body between the ribs and the pelvis (flank), shoulder, or upper arm. See Figure B.
- Apply your NEUPRO patch to a different place on your skin each day, for example, from the right side to the left side and from the upper body to the lower body. Your NEUPRO patch should not be applied to the same area of your skin more than 1 time every 14 days. Apply NEUPRO to a different area of skin (only one of the shaded areas in Figure B)each day to reduce the chance of getting skin irritation.
- If you need to apply your NEUPRO patch to a hairy area, the area should be shaved at least 3 days before applying the patch.
- Avoid applying your NEUPRO patch to areas where it could be rubbed by tight clothing or under a waistband.
- Avoid applying your NEUPRO patch on skin folds.
- Do notapply your NEUPRO patch to skin that is red, irritated, or injured.
- Avoid applying creams, lotions, ointments, oils, and powders to the skin area where your NEUPRO patch will be placed.

How to apply NEUPRO:

Step 1. | Grasp the two sides of the pouch and pull apart. See Figures Cand D.

Step 2. | Remove your NEUPRO patch from the pouch. See Figure E.

Step 3. | Hold your NEUPRO patch with both hands, with the protective liner on top. See Figure F.

Step 4. | Bend the edges of your NEUPRO patch away from you so that the S-shaped cut in the liner opens up. See Figure G.

Step 5. | Peel off one half of the protective liner. Do nottouch the sticky surface of your NEUPRO patch because the medicine could come off on your fingers. See Figure H.

Step 6. | Apply the sticky half of your NEUPRO patch to a clean area of your skin and remove the remaining liner. See Figures Iand J.

Step 7. | Press your NEUPRO patch firmly with the palm of your hand for 30seconds to make sure there is good contact with your skin, especially around the edges. The warmth of your hand helps the adhesive on the patch to stick to your skin. Make sure that your NEUPRO patch is flat against your skin. There should be no bumps or folds in your NEUPRO patch. See Figure K.

Step 8. | Wash your hands with soap and water right after handling your NEUPRO patch to remove any medicine that may have gotten on them. Do nottouch your eyes until after you have washed your hands.

How to remove NEUPRO:

- Slowly and carefully peel off your used NEUPRO patch. Carefully fold it in half (sticky sides together) and throw away the folded patch so that children and pets cannot reach it. Your NEUPRO patch still contains some medicine and could harm a child or pet.
- Gently wash the area with warm water and mild soap to remove any sticky material (adhesive) that stays on your skin.
- Baby or mineral oil may also be used to remove any adhesive. Avoid using alcohol or other solvents, such as nail polish remover. They may cause your skin to become irritated.
- Wash your hands with soap and water.
- You may see mild redness at the site when a patch is removed like when you remove an adhesive bandage. This redness should go away over time. If irritation or itchiness continues, tell your doctor.

This Patient Package Insert and Instructions for Use has been approved by the U.S. Food and Drug Administration.

Manufactured for: UCB, Inc., Smyrna, GA 30080

Neupro®is a registered trademark of the UCB Group of Companies.
©2021 UCB, Inc., Smyrna, GA 30080. All rights reserved.

Rev. 7/2021

PRINCIPAL DISPLAY PANEL - 1 mg Patch Pouch Carton

NDC 50474-801-03
30 systems

Neupro®
(rotigotine transdermal system)
1 mg/24 hours

For transdermal use only

Rx Only

PRINCIPAL DISPLAY PANEL - 1 mg Patch Pouch Carton - NDC 50474-801-17

NDC 50474-801-17
7 systems

Neupro®
(rotigotine transdermal system)

1 mg/24 hours

This package contains:

- 7 systems that deliver 1 mg/24 hours each
- Full Prescribing Information

Treatment for moderate-to-severe primary
Restless Legs Syndrome (RLS)

Please see Important Safety Information on back of carton
and full Prescribing Information inside

Sample Kit for
Restless Legs Syndrome

Professional samples – not for sale
For transdermal use only – Rx only

PRINCIPAL DISPLAY PANEL - 2 mg Patch Pouch Carton

NDC 50474-802-03
30 systems

Neupro®
(rotigotine transdermal system)
2 mg/24 hours

For transdermal use only

Rx Only

PRINCIPAL DISPLAY PANEL - 3 mg Patch Pouch Carton

NDC 50474-803-03
30 systems

Neupro®
(rotigotine transdermal system)
3 mg/24 hours

For transdermal use only

Rx Only

PRINCIPAL DISPLAY PANEL - 4 mg Patch Pouch Carton

NDC 50474-804-03
30 systems

Neupro®
(rotigotine transdermal system)
4 mg/24 hours

For transdermal use only

Rx Only

PRINCIPAL DISPLAY PANEL - 6 mg Patch Pouch Carton

NDC 50474-805-03
30 systems

Neupro®
(rotigotine transdermal system)
6 mg/24 hours

For transdermal use only

Rx Only

PRINCIPAL DISPLAY PANEL - 8 mg Patch Pouch Carton

NDC 50474-806-03
30 systems

Neupro®
(rotigotine transdermal system)
8 mg/24 hours

For transdermal use only

Rx Only

PRINCIPAL DISPLAY PANEL - Kit Carton

Treatment for Parkinson's disease.

NDC 50474-808-11

Neupro®
(rotigotine transdermal system)

Includes:

- 7 systems that deliver 2 mg/24 hours each
- 7 systems that deliver 4 mg/24 hours each

Titration kit for
Parkinson's disease

Please see Important Safety Information on back of carton
and full Prescribing Information inside.

Your step-by-step guide to beginning therapy
with the NEUPRO transdermal system

This package also contains:

- Full Prescribing Information

Professional samples—Rx only
Not for sale
For transdermal use only